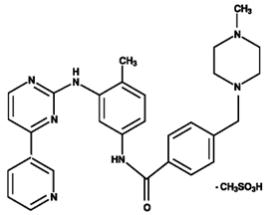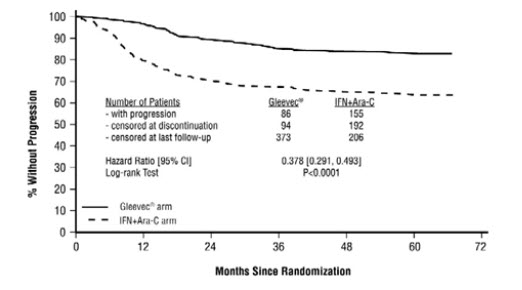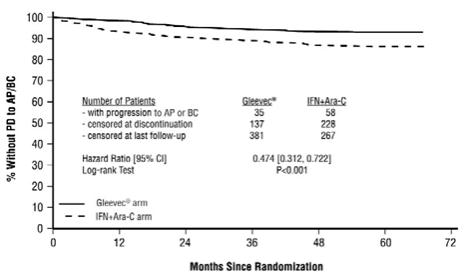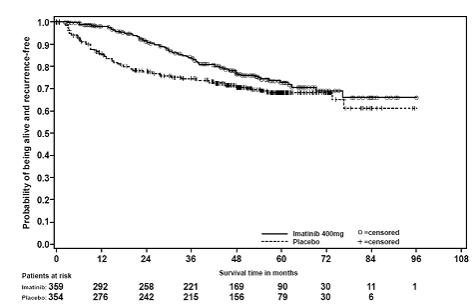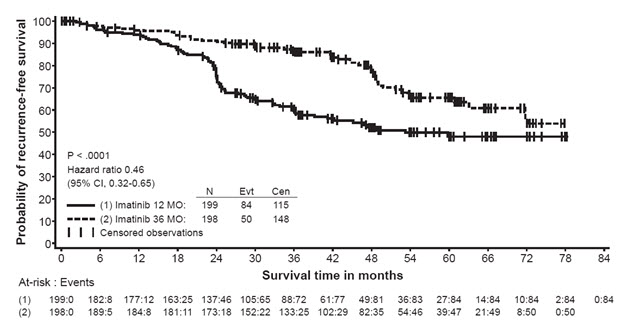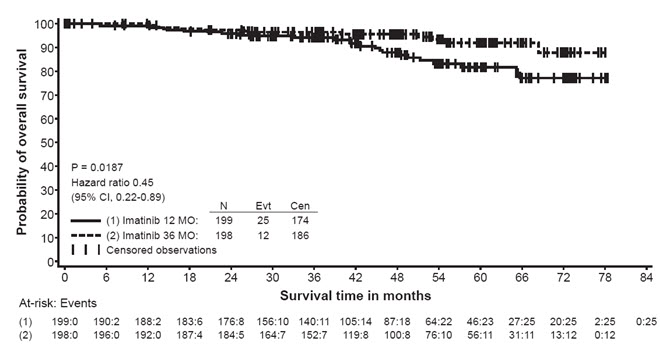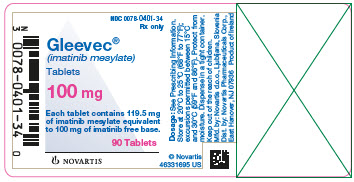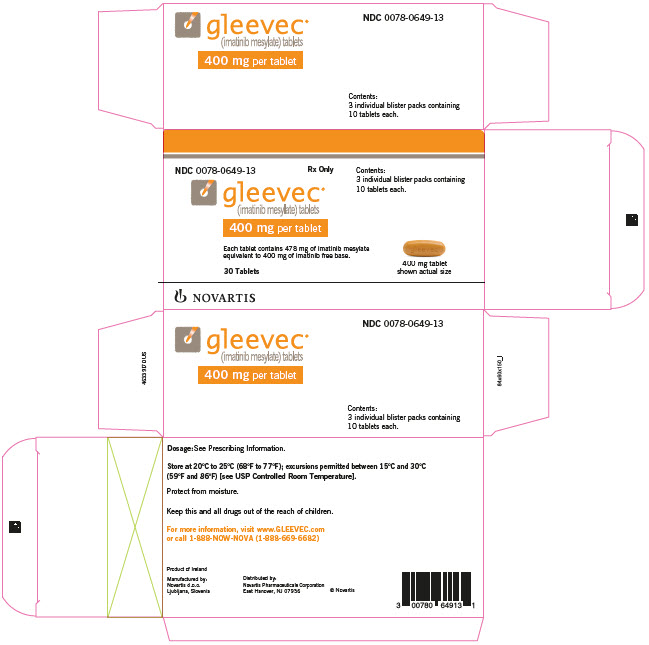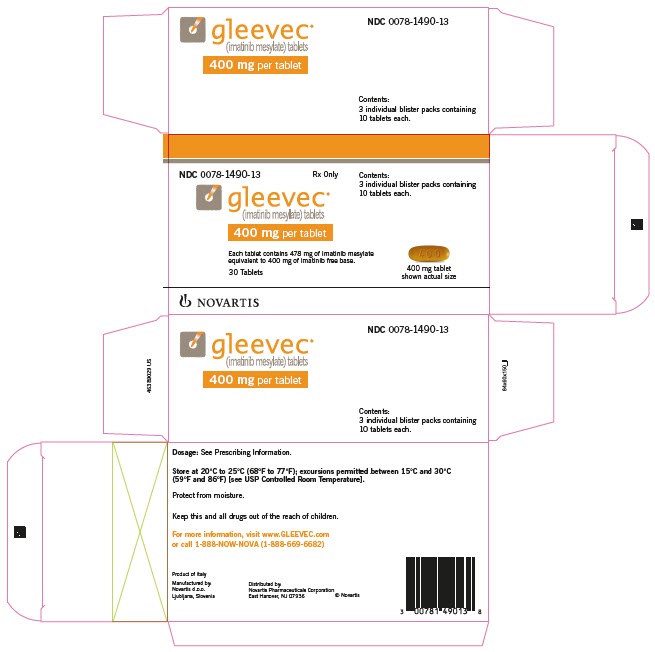 DRUG LABEL: Gleevec
NDC: 0078-0401 | Form: TABLET
Manufacturer: Novartis Pharmaceuticals Corporation
Category: prescription | Type: HUMAN PRESCRIPTION DRUG LABEL
Date: 20260218

ACTIVE INGREDIENTS: IMATINIB MESYLATE 100 mg/1 1
INACTIVE INGREDIENTS: SILICON DIOXIDE; CROSPOVIDONE; FERRIC OXIDE RED; MAGNESIUM STEARATE; CELLULOSE, MICROCRYSTALLINE; POLYETHYLENE GLYCOL 4000; TALC; HYPROMELLOSES; FERRIC OXIDE YELLOW; WATER

HIGHLIGHTS OF PRESCRIBING INFORMATION

These highlights do not include all the information needed to use GLEEVEC safely and effectively. See full prescribing information for GLEEVEC.
GLEEVEC® (imatinib mesylate) tablets, for oral use
Initial U.S. Approval: 2001

1 INDICATIONS AND USAGE

Gleevec is a kinase inhibitor indicated for the treatment of:

- Newly diagnosed adult and pediatric patients with Philadelphia chromosome positive chronic myeloid leukemia (Ph+ CML) in chronic phase. (1.1)
- Patients with Philadelphia chromosome positive chronic myeloid leukemia (Ph+ CML) in blast crisis (BC), accelerated phase (AP), or in chronic phase (CP) after failure of interferon-alpha therapy. (1.2)
- Adult patients with relapsed or refractory Philadelphia chromosome positive acute lymphoblastic leukemia (Ph+ ALL). (1.3)
- Pediatric patients with newly diagnosed Philadelphia chromosome positive acute lymphoblastic leukemia (Ph+ ALL) in combination with chemotherapy. (1.4)
- Adult patients with myelodysplastic/myeloproliferative diseases (MDS/MPD) associated with platelet-derived growth factor receptor (PDGFR) gene re-arrangements. (1.5)
- Adult patients with aggressive systemic mastocytosis (ASM) without the D816V c-Kit mutation or with c-Kit mutational status unknown. (1.6)
- Adult patients with hypereosinophilic syndrome (HES) and/or chronic eosinophilic leukemia (CEL) who have the FIP1L1-PDGFRα fusion kinase (mutational analysis or fluorescence in situ hybridization [FISH] demonstration of CHIC2 allele deletion) and for patients with HES and/or CEL who are FIP1L1-PDGFRα fusion kinase negative or unknown. (1.7)
- Adult patients with unresectable, recurrent and/or metastatic dermatofibrosarcoma protuberans (DFSP). (1.8)
- Patients with Kit (CD117) positive unresectable and/or metastatic malignant gastrointestinal stromal tumors (GIST). (1.9)
- Adjuvant treatment of adult patients following resection of Kit (CD117) positive GIST. (1.10)

2 DOSAGE AND ADMINISTRATION

- Adults with Ph+ CML CP (2.2): 400 mg/day
- Adults with Ph+ CML AP or BC (2.2): 600 mg/day
- Pediatrics with Ph+ CML CP (2.3): 340 mg/m^2/day
- Adults with Ph+ ALL (2.4): 600 mg/day
- Pediatrics with Ph+ ALL (2.5): 340 mg/m^2/day
- Adults with MDS/MPD (2.6): 400 mg/day
- Adults with ASM (2.7): 100 mg/day or 400 mg/day
- Adults with HES/CEL (2.8): 100 mg/day or 400 mg/day
- Adults with DFSP (2.9): 800 mg/day
- Adults with metastatic and/or unresectable GIST (2.10): 400 mg/day
- Adjuvant treatment of adults with GIST (2.11): 400 mg/day
- Patients with mild to moderate hepatic impairment (2.12): 400 mg/day
- Patients with severe hepatic impairment (2.12): 300 mg/day

All doses of Gleevec should be taken with a meal and a large glass of water. Doses of 400 mg or 600 mg should be administered once daily, whereas a dose of 800 mg should be administered as 400 mg twice a day. Gleevec can be dissolved in water or apple juice for patients having difficulty swallowing. Daily dosing of 800 mg and above should be accomplished using the 400-mg tablet to reduce exposure to iron.

3 DOSAGE FORMS AND STRENGTHS

Tablets (scored): 100 mg and 400 mg

4 CONTRAINDICATIONS

None. (4)

5 WARNINGS AND PRECAUTIONS

- Edema and severe fluid retention have occurred. Weigh patients regularly and manage unexpected rapid weight gain by drug interruption and diuretics. (5.1, 6.1)
- Cytopenias, particularly anemia, neutropenia, and thrombocytopenia, have occurred. Manage with dose reduction, dose interruption, or discontinuation of treatment. Perform complete blood counts weekly for the first month, biweekly for the second month, and periodically thereafter. (5.2)
- Severe congestive heart failure and left ventricular dysfunction have been reported, particularly in patients with comorbidities and risk factors. Monitor and treat patients with cardiac disease or risk factors for cardiac failure. (5.3)
- Severe hepatotoxicity, including fatalities may occur. Assess liver function before initiation of treatment and monthly thereafter or as clinically indicated. Monitor liver function when combined with chemotherapy known to be associated with liver dysfunction. (5.4)
- Grade 3/4 hemorrhage has been reported in clinical studies in patients with newly diagnosed CML and with GIST. GI tumor sites may be the source of GI bleeds in GIST. (5.5)
- Gastrointestinal (GI) perforations, some fatal, have been reported. (5.6)
- Cardiogenic shock/left ventricular dysfunction has been associated with the initiation of Gleevec in patients with conditions associated with high eosinophil levels (e.g., HES, MDS/MPD, and ASM). (5.7)
- Bullous dermatologic reactions (e.g., erythema multiforme and Stevens-Johnson syndrome) have been reported with the use of Gleevec. (5.8)
- Hypothyroidism has been reported in thyroidectomy patients undergoing levothyroxine replacement. Closely monitor TSH levels in such patients. (5.9)
- Fetal harm can occur when administered to a pregnant woman. Apprise women of the potential harm to the fetus, and to use effective contraception. (5.10, 8.1)
- Growth retardation occurring in children and pre-adolescents receiving Gleevec has been reported. Close monitoring of growth in children under Gleevec treatment is recommended. (5.11, 6.2)
- Tumor Lysis Syndrome. Close monitoring is recommended. (5.12)
- Reports of motor vehicle accidents have been received in patients receiving Gleevec. Caution patients about driving a car or operating machinery. (5.13)
- Renal Toxicity. A decline in renal function may occur in patients receiving Gleevec. Evaluate renal function at baseline and during therapy, with attention to risk factors for renal dysfunction. (5.14)

6 ADVERSE REACTIONS

The most frequently reported adverse reactions (greater than or equal to 30%) are edema, nausea, vomiting, muscle cramps, musculoskeletal pain, diarrhea, rash, fatigue, and abdominal pain. (6.1)

To report SUSPECTED ADVERSE REACTIONS, contact Novartis Pharmaceuticals Corporation at 1-888-669-6682 or FDA at 1-800-FDA-1088 or www.fda.gov/medwatch.

7 DRUG INTERACTIONS

- CYP3A4 inducers may decrease Gleevec Cmax and area under curve (AUC). (2.12, 7.1, 12.3)
- CYP3A4 inhibitors may increase Gleevec Cmax and AUC. (7.2, 12.3)
- Gleevec is an inhibitor of CYP3A4 and CYP2D6 which may increase the Cmax and AUC of other drugs. (7.3, 7.4, 12.3)
- Patients who require anticoagulation should receive low-molecular weight or standard heparin and not warfarin. (7.3)
- Gleevec may delay the clearance of methotrexate when methotrexate is used at high doses (> 500 mg/m^2). (7.5)

FULL PRESCRIBING INFORMATION

1 INDICATIONS AND USAGE

1.1 Newly Diagnosed Philadelphia Positive Chronic Myeloid Leukemia (Ph+ CML)

Newly diagnosed adult and pediatric patients with Philadelphia chromosome positive chronic myeloid leukemia (Ph+ CML) in chronic phase.

1.2 Ph+ CML in Blast Crisis (BC), Accelerated Phase (AP) or Chronic Phase (CP) After Interferon-alpha (IFN) Therapy

Patients with Philadelphia chromosome positive chronic myeloid leukemia in blast crisis, accelerated phase, or in chronic phase after failure of interferon-alpha therapy.

1.3 Adult Patients With Ph+ Acute Lymphoblastic Leukemia (ALL)

Adult patients with relapsed or refractory Philadelphia chromosome positive acute lymphoblastic leukemia (Ph+ ALL).

1.4 Pediatric Patients With Ph+ Acute Lymphoblastic Leukemia (ALL)

Pediatric patients with newly diagnosed Philadelphia chromosome positive acute lymphoblastic leukemia (Ph+ ALL) in combination with chemotherapy.

1.5 Myelodysplastic/Myeloproliferative Diseases (MDS/MPD)

Adult patients with myelodysplastic/myeloproliferative diseases associated with platelet-derived growth factor receptor (PDGFR) gene re-arrangements.

1.6 Aggressive Systemic Mastocytosis (ASM)

Adult patients with aggressive systemic mastocytosis without the D816V c-Kit mutation or with c-Kit mutational status unknown.

1.7 Hypereosinophilic Syndrome (HES) and/or Chronic Eosinophilic Leukemia (CEL)

Adult patients with hypereosinophilic syndrome and/or chronic eosinophilic leukemia who have the FIP1L1-PDGFRα fusion kinase (mutational analysis or fluorescence in situ hybridization [FISH] demonstration of CHIC2 allele deletion) and for patients with HES and/or CEL who are FIP1L1-PDGFRα fusion kinase negative or unknown.

1.8 Dermatofibrosarcoma Protuberans (DFSP)

Adult patients with unresectable, recurrent and/or metastatic dermatofibrosarcoma protuberans.

1.9 Kit+ Gastrointestinal Stromal Tumors (GIST)

Patients with Kit (CD117) positive unresectable and/or metastatic malignant gastrointestinal stromal tumors.

1.10 Adjuvant Treatment of GIST

Adjuvant treatment of adult patients following complete gross resection of Kit (CD117) positive GIST.

2 DOSAGE AND ADMINISTRATION

2.1 Drug Administration

The prescribed dose should be administered orally, with a meal and a large glass of water. Doses of 400 mg or 600 mg should be administered once daily, whereas a dose of 800 mg should be administered as 400 mg twice a day.

For patients unable to swallow the film-coated tablets, the tablets may be dispersed in a glass of water or apple juice. The required number of tablets should be placed in the appropriate volume of beverage (approximately 50 mL for a 100-mg tablet, and 200 mL for a 400-mg tablet) and stirred with a spoon. The suspension should be administered immediately after complete disintegration of the tablet(s).

For daily dosing of 800 mg and above, dosing should be accomplished using the 400-mg tablet to reduce exposure to iron.

Treatment may be continued as long as there is no evidence of progressive disease or unacceptable toxicity.

2.2 Adult Patients With Ph+ CML CP, AP, or BC

The recommended dose of Gleevec is 400 mg/day for adult patients in chronic phase CML and 600 mg/day for adult patients in accelerated phase or blast crisis.

In CML, a dose increase from 400 mg to 600 mg in adult patients with chronic phase disease, or from 600 mg to 800 mg (given as 400 mg twice daily) in adult patients in accelerated phase or blast crisis may be considered in the absence of severe adverse drug reaction and severe non-leukemia related neutropenia or thrombocytopenia in the following circumstances: disease progression (at any time), failure to achieve a satisfactory hematologic response after at least 3 months of treatment, failure to achieve a cytogenetic response after 6 to 12 months of treatment, or loss of a previously achieved hematologic or cytogenetic response.

2.3 Pediatric Patients With Ph+ CML CP

The recommended dose of Gleevec for children with newly diagnosed Ph+ CML is 340 mg/m^2/day (not to exceed 600 mg). Gleevec treatment can be given as a once daily dose or the daily dose may be split into two–one portion dosed in the morning and one portion in the evening. There is no experience with Gleevec treatment in children under 1 year of age.

2.4 Adult Patients With Ph+ ALL

The recommended dose of Gleevec is 600 mg/day for adult patients with relapsed/refractory Ph+ ALL.

2.5 Pediatric Patients With Ph+ ALL

The recommended dose of Gleevec to be given in combination with chemotherapy to children with newly diagnosed Ph+ ALL is 340 mg/m^2/day (not to exceed 600 mg). Gleevec treatment can be given as a once daily dose.

2.6 Adult Patients With MDS/MPD

Determine PDGFRb gene rearrangements status prior to initiating treatment.

The recommended dose of Gleevec is 400 mg/day for adult patients with MDS/MPD.

2.7 Adult Patients With ASM

Determine D816V c-Kit mutation status prior to initiating treatment.

The recommended dose of Gleevec is 400 mg/day for adult patients with ASM without the D816V c-Kit mutation. If c-Kit mutational status is not known or unavailable, treatment with Gleevec 400 mg/day may be considered for patients with ASM not responding satisfactorily to other therapies. For patients with ASM associated with eosinophilia, a clonal hematological disease related to the fusion kinase FIP1L1-PDGFRα, a starting dose of 100 mg/day is recommended. Dose increase from 100 mg to 400 mg for these patients may be considered in the absence of adverse drug reactions if assessments demonstrate an insufficient response to therapy.

2.8 Adult Patients With HES/CEL

The recommended dose of Gleevec is 400 mg/day for adult patients with HES/CEL. For HES/CEL patients with demonstrated FIP1L1-PDGFRα fusion kinase, a starting dose of 100 mg/day is recommended. Dose increase from 100 mg to 400 mg for these patients may be considered in the absence of adverse drug reactions if assessments demonstrate an insufficient response to therapy.

2.9 Adult Patients With DFSP

The recommended dose of Gleevec is 800 mg/day for adult patients with DFSP.

2.10 Adult Patients With Metastatic and/or Unresectable GIST

The recommended dose of Gleevec is 400 mg/day for adult patients with unresectable and/or metastatic, malignant GIST. A dose increase up to 800 mg daily (given as 400 mg twice daily) may be considered, as clinically indicated, in patients showing clear signs or symptoms of disease progression at a lower dose and in the absence of severe adverse drug reactions.

2.11 Adult Patients With Adjuvant GIST

The recommended dose of Gleevec is 400 mg/day for the adjuvant treatment of adult patients following complete gross resection of GIST. In clinical trials, one year of Gleevec and three years of Gleevec were studied. In the patient population defined in Study 2, three years of Gleevec is recommended [see Clinical Studies (14.8)]. The optimal treatment duration with Gleevec is not known.

2.12 Dose Modification Guidelines

Concomitant Strong CYP3A4 inducers: The use of concomitant strong CYP3A4 inducers should be avoided (e.g., dexamethasone, phenytoin, carbamazepine, rifampin, rifabutin, rifampacin, phenobarbital). If patients must be coadministered a strong CYP3A4 inducer, based on pharmacokinetic studies, the dosage of Gleevec should be increased by at least 50%, and clinical response should be carefully monitored [see Drug Interactions (7.1)].

Hepatic Impairment: Patients with mild and moderate hepatic impairment do not require a dose adjustment and should be treated per the recommended dose. A 25% decrease in the recommended dose should be used for patients with severe hepatic impairment [see Use in Specific Populations (8.6)].

Renal Impairment: Patients with moderate renal impairment (creatinine clearance [CrCL] = 20-39 mL/min) should receive a 50% decrease in the recommended starting dose and future doses can be increased as tolerated. Doses greater than 600 mg are not recommended in patients with mild renal impairment (CrCL = 40-59 mL/min). For patients with moderate renal impairment doses greater than 400 mg are not recommended.

Imatinib should be used with caution in patients with severe renal impairment. A dose of 100 mg/day was tolerated in two patients with severe renal impairment [see Warnings and Precautions (5.3), Use in Specific Populations (8.7)].

2.13 Dose Adjustment for Hepatotoxicity and Non-Hematologic Adverse Reactions

If elevations in bilirubin greater than 3 times the institutional upper limit of normal (IULN) or in liver transaminases greater than 5 times the IULN occur, Gleevec should be withheld until bilirubin levels have returned to a less than 1.5 times the IULN and transaminase levels to less than 2.5 times the IULN. In adults, treatment with Gleevec may then be continued at a reduced daily dose (i.e., 400 mg to 300 mg, 600 mg to 400 mg, or 800 mg to 600 mg). In children, daily doses can be reduced under the same circumstances from 340 mg/m^2/day to 260 mg/m^2/day.

If a severe non-hematologic adverse reaction develops (such as severe hepatotoxicity or severe fluid retention), Gleevec should be withheld until the event has resolved. Thereafter, treatment can be resumed as appropriate depending on the initial severity of the event.

2.14 Dose Adjustment for Hematologic Adverse Reactions

Dose reduction or treatment interruptions for severe neutropenia and thrombocytopenia are recommended as indicated in Table 1.

Table 1: Dose Adjustments for Neutropenia and Thrombocytopenia
ASM associated with eosinophilia (starting dose 100 mg) | ANC less than 1 x 10^9/L and/or platelets less than 50 x 10^9/L | 1. Stop Gleevec until ANC greater than or equal to 1.5 x 10^9/L and platelets greater than or equal to 75 x 10^9/L 2. Resume treatment with Gleevec at previous dose (i.e., dose before severe adverse reaction)
HES/CEL with FIP1L1-PDGFRα fusion kinase (starting dose 100 mg) | ANC less than 1 x 10^9/L and/or platelets less than 50 x 10^9/L | 1. Stop Gleevec until ANC greater than or equal to 1.5 x 10^9/L and platelets greater than or equal to 75 x 10^9/L 2. Resume treatment with Gleevec at previous dose (i.e., dose before severe adverse reaction)
Chronic Phase CML (starting dose 400 mg) MDS/MPD, ASM and HES/CEL (starting dose 400 mg) GIST (starting dose 400 mg) | ANC less than 1 x 10^9/L and/or platelets less than 50 x 10^9/L | 1. Stop Gleevec until ANC greater than or equal to 1.5 x 10^9/L and platelets greater than or equal to 75 x 10^9/L 2. Resume treatment with Gleevec at the original starting dose of 400 mg 3. If recurrence of ANC less than 1 x 10^9/L and/or platelets less than 50 x 10^9/L, repeat step 1 and resume Gleevec at a reduced dose of 300 mg
Ph+ CML: Accelerated Phase and Blast Crisis (starting dose 600 mg) Ph+ ALL (starting dose 600 mg) | ANC less than 0.5 x 10^9/L and/or platelets less than 10 x 10^9/L | 1. Check if cytopenia is related to leukemia (marrow aspirate or biopsy) 2. If cytopenia is unrelated to leukemia, reduce dose of Gleevec to 400 mg 3. If cytopenia persists 2 weeks, reduce further to 300 mg 4. If cytopenia persists 4 weeks and is still unrelated to leukemia, stop Gleevec until ANC greater than or equal to 1 x 10^9/L and platelets greater than or equal to 20 x 10^9/L and then resume treatment at 300 mg
DFSP (starting dose 800 mg) | ANC less than 1 x 10^9/L and/or platelets less than 50 x 10^9/L | 1. Stop Gleevec until ANC greater than or equal to 1.5 x 10^9/L and platelets greater than or equal to 75 x 10^9/L 2. Resume treatment with Gleevec at 600 mg 3. In the event of recurrence of ANC less than 1 x 10^9/L and/or platelets less than 50 x 10^9/L, repeat step 1 and resume Gleevec at reduced dose of 400 mg
Pediatric newly diagnosed chronic phase CML (starting dose 340 mg/m^2) | ANC less than 1 x 10^9/L and/or platelets less than 50 x 10^9/L | 1. Stop Gleevec until ANC greater than or equal to 1.5 x 10^9/L and platelets greater than or equal to 75 x 10^9/L 2. Resume treatment with Gleevec at previous dose (i.e., dose before severe adverse reaction) 3. In the event of recurrence of ANC less than 1 x 10^9/L and/or platelets less than 50 x 10^9/L, repeat step 1 and resume Gleevec at reduced dose of 260 mg/m^2
Abbreviations: ANC, absolute neutrophil count; ASM, aggressive systemic mastocytosis; CEL, chronic eosinophilic leukemia; CML, chronic myeloid leukemia; DFSP, dermatofibrosarcoma protuberans; HES, hypereosinophilic syndrome; MDS/MPD, myelodysplastic/myeloproliferative diseases; PDGFR, platelet-derived growth factor receptor; Ph+ CML, Philadelphia chromosome positive chronic myeloid leukemia; Ph+ ALL, Philadelphia chromosome positive acute lymphoblastic leukemia.

3 DOSAGE FORMS AND STRENGTHS

- 100 mg film coated tablets

Very dark yellow to brownish orange, film-coated tablets, round, biconvex with bevelled edges, debossed with “NVR” on one side, and “SA” with score on the other side

- 400 mg film coated tablets

Very dark yellow to brownish orange, film-coated tablets, ovaloid, biconvex with bevelled edges, debossed with “gleevec” on one side and score on the other side.

Very dark yellow to brownish orange, film-coated tablets, ovaloid, biconvex with bevelled edges, debossed with “400” on one side and score on the other side with “SL” on each side of the score.

4 CONTRAINDICATIONS

None.

5 WARNINGS AND PRECAUTIONS

5.1 Fluid Retention and Edema

Gleevec is often associated with edema and occasionally serious fluid retention [see Adverse Reactions (6.1)]. Weigh and monitor patients regularly for signs and symptoms of fluid retention. Investigate unexpected rapid weight gain carefully and provide appropriate treatment. The probability of edema was increased with higher Gleevec dose and age greater than 65 years in the CML studies. Severe superficial edema was reported in 1.5% of newly diagnosed CML patients taking Gleevec, and in 2% to 6% of other adult CML patients taking Gleevec. In addition, other severe fluid retention (e.g., pleural effusion, pericardial effusion, pulmonary edema, and ascites) reactions were reported in 1.3% of newly diagnosed CML patients taking Gleevec, and in 2% to 6% of other adult CML patients taking Gleevec. Severe fluid retention was reported in 9% to 13.1% of patients taking Gleevec for GIST [see Adverse Reactions (6.1)]. In a randomized trial in patients with newly diagnosed Ph+ CML in chronic phase comparing Gleevec and nilotinib, severe (Grade 3 or 4) fluid retention occurred in 2.5% of patients receiving Gleevec and in 3.9% of patients receiving nilotinib 300 mg twice daily. Effusions (including pleural effusion, pericardial effusion, ascites) or pulmonary edema were observed in 2.1% (none were Grade 3 or 4) of patients in the Gleevec arm and 2.2% (0.7% Grade 3 or 4) of patients in the nilotinib 300 mg twice daily arm.

5.2 Hematologic Toxicity

Treatment with Gleevec is associated with anemia, neutropenia, and thrombocytopenia. Perform complete blood counts weekly for the first month, biweekly for the second month, and periodically thereafter as clinically indicated (for example, every 2 to 3 months). In CML, the occurrence of these cytopenias is dependent on the stage of disease and is more frequent in patients with accelerated phase CML or blast crisis than in patients with chronic phase CML. In pediatric CML patients the most frequent toxicities observed were Grade 3 or 4 cytopenias, including neutropenia, thrombocytopenia, and anemia. These generally occur within the first several months of therapy [see Dosage and Administration (2.14)].

5.3 Congestive Heart Failure and Left Ventricular Dysfunction

Congestive heart failure and left ventricular dysfunction have been reported in patients taking Gleevec. Cardiac adverse reactions were more frequent in patients with advanced age or co-morbidities, including previous medical history of cardiac disease. In an international randomized Phase 3 study in 1106 patients with newly diagnosed Ph+ CML in chronic phase, severe cardiac failure and left ventricular dysfunction were observed in 0.7% of patients taking Gleevec compared to 0.9% of patients taking IFN + Ara-C. In another randomized trial with newly diagnosed Ph+ CML patients in chronic phase that compared Gleevec and nilotinib, cardiac failure was observed in 1.1% of patients in the Gleevec arm and 2.2% of patients in the nilotinib 300 mg twice daily arm and severe (Grade 3 or 4) cardiac failure occurred in 0.7% of patients in each group. Carefully monitor patients with cardiac disease or risk factors for cardiac or history of renal failure. Evaluate and treat any patient with signs or symptoms consistent with cardiac or renal failure.

5.4 Hepatotoxicity

Hepatotoxicity, occasionally severe, may occur with Gleevec [see Adverse Reactions (6.1)]. Cases of fatal liver failure and severe liver injury requiring liver transplants have been reported with both short-term and long-term use of Gleevec. Monitor liver function (transaminases, bilirubin, and alkaline phosphatase) before initiation of treatment and monthly, or as clinically indicated. Manage laboratory abnormalities with Gleevec interruption and/or dose reduction [see Dosage and Administration (2.13)]. When Gleevec is combined with chemotherapy, liver toxicity in the form of transaminase elevation and hyperbilirubinemia has been observed. Additionally, there have been reports of acute liver failure. Monitoring of hepatic function is recommended.

5.5 Hemorrhage

In a trial of Gleevec versus IFN+Ara-C in patients with the newly diagnosed CML, 1.8% of patients had Grade 3/4 hemorrhage. In the Phase 3 unresectable or metastatic GIST studies, 211 patients (12.9%) reported Grade 3/4 hemorrhage at any site. In the Phase 2 unresectable or metastatic GIST study, 7 patients (5%) had a total of 8 CTC Grade 3/4 hemorrhages; gastrointestinal (GI) (3 patients), intra-tumoral (3 patients) or both (1 patient). Gastrointestinal tumor sites may have been the source of GI hemorrhages. In a randomized trial in patients with newly diagnosed Ph+ CML in chronic phase comparing Gleevec and nilotinib, GI hemorrhage occurred in 1.4% of patients in the Gleevec arm, and in 2.9% of patients in the nilotinib 300 mg twice daily arm. None of these events were Grade 3 or 4 in the Gleevec arm; 0.7% were Grade 3 or 4 in the nilotinib 300 mg twice daily arm. In addition, gastric antral vascular ectasia has been reported in postmarketing experience.

5.6 Gastrointestinal Disorders

Gleevec is sometimes associated with GI irritation. Gleevec should be taken with food and a large glass of water to minimize this problem. There have been rare reports, including fatalities, of GI perforation.

5.7 Hypereosinophilic Cardiac Toxicity

In patients with hypereosinophilic syndrome with occult infiltration of HES cells within the myocardium, cases of cardiogenic shock/left ventricular dysfunction have been associated with HES cell degranulation upon the initiation of Gleevec therapy. The condition was reported to be reversible with the administration of systemic steroids, circulatory support measures and temporarily withholding Gleevec.

Myelodysplastic/myeloproliferative disease and systemic mastocytosis may be associated with high eosinophil levels. Consider performing an echocardiogram and determining serum troponin in patients with HES/CEL, and in patients with MDS/MPD or ASM associated with high eosinophil levels. If either is abnormal, consider prophylactic use of systemic steroids (1-2 mg/kg) for one to two weeks concomitantly with Gleevec at the initiation of therapy.

5.8 Dermatologic Toxicities

Bullous dermatologic reactions, including erythema multiforme and Stevens-Johnson syndrome, have been reported with use of Gleevec. In some cases of bullous dermatologic reactions, including erythema multiforme and Stevens-Johnson syndrome reported during postmarketing surveillance, a recurrent dermatologic reaction was observed upon rechallenge. Several foreign postmarketing reports have described cases in which patients tolerated the reintroduction of Gleevec therapy after resolution or improvement of the bullous reaction. In these instances, Gleevec was resumed at a dose lower than that at which the reaction occurred and some patients also received concomitant treatment with corticosteroids or antihistamines.

5.9 Hypothyroidism

Clinical cases of hypothyroidism have been reported in thyroidectomy patients undergoing levothyroxine replacement during treatment with Gleevec. Monitor TSH levels in such patients.

5.10 Embryo-Fetal Toxicity

Gleevec can cause fetal harm when administered to a pregnant woman. Imatinib mesylate was teratogenic in rats when administered during organogenesis at doses approximately equal to the maximum human dose of 800 mg/day based on body surface area (BSA). Significant post-implantation loss was seen in female rats administered imatinib mesylate at doses approximately one-half the maximum human dose of 800 mg/day based on BSA. Advise sexually active female patients of reproductive potential to use effective contraception (methods that result in less than 1% pregnancy rates) when using Gleevec and for 14 days after stopping Gleevec. If this drug is used during pregnancy or if the patient becomes pregnant while taking this drug, apprise the patient of the potential hazard to a fetus [see Use in Specific Populations (8.1)].

5.11 Growth Retardation in Children and Adolescents

Growth retardation has been reported in children and pre-adolescents receiving Gleevec. The long-term effects of prolonged treatment with Gleevec on growth in children are unknown. Therefore, monitor growth in children under Gleevec treatment [see Adverse Reactions (6.1)].

5.12 Tumor Lysis Syndrome

Cases of Tumor Lysis Syndrome (TLS), including fatal cases, have been reported in patients with CML, GIST, ALL, and eosinophilic leukemia receiving Gleevec. The patients at risk of TLS are those with tumors having a high proliferative rate or high tumor burden prior to treatment. Monitor these patients closely and take appropriate precautions. Due to possible occurrence of TLS, correct clinically significant dehydration and treat high uric acid levels prior to initiation of Gleevec.

5.13 Impairments Related to Driving and Using Machinery

Motor vehicle accidents have been reported in patients receiving Gleevec. Advise patients that they may experience side effects, such as dizziness, blurred vision, or somnolence during treatment with Gleevec. Recommend caution when driving a car or operating machinery.

5.14 Renal Toxicity

A decline in renal function may occur in patients receiving Gleevec. Median estimated glomerular filtration rate (eGFR) values in patients on Gleevec 400 mg daily for newly-diagnosed CML (four randomized trials) and malignant GIST (one single-arm trial) declined from a baseline value of 85 mL/min/1.73 m^2 (N = 1190) to 75 mL/min/1.73 m^2 at 12 months (N = 1082) and 69 mL/min/1.73 m^2 at 60 months (N = 549). Evaluate renal function prior to initiating Gleevec and monitor during therapy, with attention to risk factors for renal dysfunction, such as preexisting renal impairment, diabetes mellitus, hypertension, and congestive heart failure.

6 ADVERSE REACTIONS

The following serious adverse reactions are described elsewhere in the labeling:

- Fluid Retention and Edema [see Warnings and Precautions (5.1)]
- Hematologic Toxicity [see Warnings and Precautions (5.2)]
- Congestive Heart Failure and Left Ventricular Dysfunction [see Warnings and Precautions (5.3)]
- Hepatotoxicity [see Warnings and Precautions (5.4)]
- Hemorrhage [see Warnings and Precautions (5.5)]
- Gastrointestinal Disorders [see Warnings and Precautions (5.6)]
- Hypereosinophilic Cardiac Toxicity [see Warnings and Precautions (5.7)]
- Dermatologic Toxicities [see Warnings and Precautions (5.8)]
- Hypothyroidism [see Warnings and Precautions (5.9)]
- Growth Retardation in Children and Adolescents [see Warnings and Precautions (5.11)]
- Tumor Lysis Syndrome [see Warnings and Precautions (5.12)]
- Impairments Related to Driving and Using Machinery [see Warnings and Precautions (5.13)]
- Renal Toxicity [see Warnings and Precautions (5.14)]

6.1 Clinical Trials Experience

Because clinical trials are conducted under widely varying conditions, adverse reaction rates observed in the clinical trials of a drug cannot be directly compared to rates in the clinical trials of another drug and may not reflect the rates observed in practice.

Chronic Myeloid Leukemia

The majority of Gleevec-treated patients experienced adverse reactions at some time. Gleevec was discontinued due to drug-related adverse reactions in 2.4% of patients receiving Gleevec in the randomized trial of newly diagnosed patients with Ph+ CML in chronic phase comparing Gleevec versus IFN+Ara-C, and in 12.5% of patients receiving Gleevec in the randomized trial of newly diagnosed patients with Ph+ CML in chronic phase comparing Gleevec and nilotinib. Gleevec was discontinued due to drug-related adverse reactions in 4% of patients in chronic phase after failure of interferon-alpha therapy, in 4% of patients in accelerated phase and in 5% of patients in blast crisis.

The most frequently reported drug-related adverse reactions were edema, nausea and vomiting, muscle cramps, musculoskeletal pain, diarrhea and rash (Table 2 and Table 3 for newly diagnosed CML, Table 4 for other CML patients). Edema was most frequently periorbital or in lower limbs and was managed with diuretics, other supportive measures, or by reducing the dose of Gleevec [see Dosage and Administration (2.13)]. The frequency of severe superficial edema was 1.5%-6%.

A variety of adverse reactions represent local or general fluid retention, including pleural effusion, ascites, pulmonary edema, and rapid weight gain with or without superficial edema. These reactions appear to be dose related, were more common in the blast crisis and accelerated phase studies (where the dose was 600 mg/day), and are more common in the elderly. These reactions were usually managed by interrupting Gleevec treatment and using diuretics or other appropriate supportive care measures. These reactions may be serious or life threatening.

Adverse reactions, regardless of relationship to study drug, that were reported in at least 10% of the Gleevec-treated patients are shown in Tables 2, 3, and 4.

Table 2: Adverse Reactions Regardless of Relationship to Study Drug Reported in Newly Diagnosed CML Clinical Trial in the Gleevec Versus IFN+Ara-C Study (Greater Than or Equal to 10% of Gleevec-Treated Patients)(1)
 | All Grades |  | CTC Grades* 3/4
 | Gleevec | IFN+Ara−C | Gleevec | IFN+Ara−C
Preferred term | N = 551 (%) | N = 533 (%) | N = 551 (%) | N = 533 (%)
Fluid retention | 61.7 | 11.1 | 2.5 | 0.9
− Superficial edema | 59.9 | 9.6 | 1.5 | 0.4
− Other fluid retention reactions^2 | 6.9 | 1.9 | 1.3 | 0.6
Nausea | 49.5 | 61.5 | 1.3 | 5.1
Muscle cramps | 49.2 | 11.8 | 2.2 | 0.2
Musculoskeletal pain | 47.0 | 44.8 | 5.4 | 8.6
Diarrhea | 45.4 | 43.3 | 3.3 | 3.2
Rash and related terms | 40.1 | 26.1 | 2.9 | 2.4
Fatigue | 38.8 | 67.0 | 1.8 | 25.1
Headache | 37.0 | 43.3 | 0.5 | 3.8
Joint pain | 31.4 | 38.1 | 2.5 | 7.7
Abdominal pain | 36.5 | 25.9 | 4.2 | 3.9
Nasopharyngitis | 30.5 | 8.8 | 0 | 0.4
Hemorrhage | 28.9 | 21.2 | 1.8 | 1.7
- GI hemorrhage | 1.6 | 1.1 | 0.5 | 0.2
- CNS hemorrhage | 0.2 | 0.4 | 0 | 0.4
Myalgia | 24.1 | 38.8 | 1.5 | 8.3
Vomiting | 22.5 | 27.8 | 2.0 | 3.4
Dyspepsia | 18.9 | 8.3 | 0 | 0.8
Cough | 20.0 | 23.1 | 0.2 | 0.6
Pharyngolaryngeal pain | 18.1 | 11.4 | 0.2 | 0
Upper respiratory tract infection | 21.2 | 8.4 | 0.2 | 0.4
Dizziness | 19.4 | 24.4 | 0.9 | 3.8
Pyrexia | 17.8 | 42.6 | 0.9 | 3.0
Weight increased | 15.6 | 2.6 | 2.0 | 0.4
Insomnia | 14.7 | 18.6 | 0 | 2.3
Depression | 14.9 | 35.8 | 0.5 | 13.1
Influenza | 13.8 | 6.2 | 0.2 | 0.2
Bone pain | 11.3 | 15.6 | 1.6 | 3.4
Constipation | 11.4 | 14.4 | 0.7 | 0.2
Sinusitis | 11.4 | 6.0 | 0.2 | 0.2
Abbreviations: CML, chronic myeloid leukemia; CNS, central nervous system; CTC, common terminology criteria; GI, gastrointestinal; IFN, Interferon-alpha.
*NCI Common Terminology Criteria for Adverse Events, version 3.0.
(1)All adverse reactions occurring in greater than or equal to 10% of Gleevec-treated patients are listed regardless of suspected relationship to treatment.
(2)Other fluid retention reactions include pleural effusion, ascites, pulmonary edema, pericardial effusion, anasarca, edema aggravated, and fluid retention not otherwise specified.

Table 3: Most Frequently Reported Non-Hematologic Adverse Reactions (regardless of relationship to study drug) in Patients With Newly Diagnosed Ph+ CML-CP in the Gleevec Versus Nilotinib Study (Greater Than or Equal to 10% in Gleevec 400 mg Once Daily or Nilotinib 300 mg Twice Daily Groups) 60-Month Analysisa
 |  | Patients with newly diagnosed Ph+ CML-CP
 |  | Gleevec 400 mg once daily | Nilotinib 300 mg twice daily | Gleevec 400 mg once daily | Nilotinib 300 mg twice daily
 |  | N = 280 | N = 279 | N = 280 | N = 279
Body system and preferred term |  | All Grades (%) |  | CTC Gradesb 3/4 (%)
Skin and subcutaneous tissue disorders | Rash | 19 | 38 | 2 | < 1
 | Pruritus | 7 | 21 | 0 | < 1
 | Alopecia | 7 | 13 | 0 | 0
 | Dry skin | 6 | 12 | 0 | 0
Gastrointestinal disorders | Nausea | 41 | 22 | 2 | 2
 | Constipation | 8 | 20 | 0 | < 1
 | Diarrhea | 46 | 19 | 4 | 1
 | Vomiting | 27 | 15 | < 1 | < 1
 | Abdominal pain upper | 14 | 18 | < 1 | 1
 | Abdominal pain | 12 | 15 | 0 | 2
 | Dyspepsia | 12 | 10 | 0 | 0
Nervous system disorders | Headache | 23 | 32 | < 1 | 3
 | Dizziness | 11 | 12 | < 1 | < 1
General disorders and administration-site conditions | Fatigue | 20 | 23 | 1 | 1
 | Pyrexia | 13 | 14 | 0 | < 1
 | Asthenia | 12 | 14 | 0 | < 1
 | Peripheral edema | 20 | 9 | 0 | < 1
 | Face edema | 14 | < 1 | < 1 | 0
Musculoskeletal and connective tissue disorders | Myalgia | 19 | 19 | < 1 | < 1
 | Arthralgia | 17 | 22 | < 1 | < 1
 | Muscle spasms | 34 | 12 | 1 | 0
 | Pain in extremity | 16 | 15 | < 1 | < 1
 | Back pain | 17 | 19 | 1 | 1
Respiratory, thoracic and mediastinal disorders | Cough | 13 | 17 | 0 | 0
 | Oropharyngeal pain | 6 | 12 | 0 | 0
 | Dyspnea | 6 | 11 | < 1 | 2
Infections and infestations | Nasopharyngitis | 21 | 27 | 0 | 0
 | Upper respiratory tract infection | 14 | 17 | 0 | < 1
 | Influenza | 9 | 13 | 0 | 0
 | Gastroenteritis | 10 | 7 | < 1 | 0
Eye disorders | Eyelid edema | 19 | 1 | < 1 | 0
 | Periorbital edema | 15 | < 1 | 0 | 0
Psychiatric disorders | Insomnia | 9 | 11 | 0 | 0
Vascular disorder | Hypertension | 4 | 10 | < 1 | 1
Abbreviation: Ph+ CML-CP, Philadelphia chromosome positive chronic myeloid leukemia-chronic phase.
aExcluding laboratory abnormalities.
bNCI Common Terminology Criteria for Adverse Events, version 3.0.

Table 4: Adverse Reactions Regardless of Relationship to Study Drug Reported in Other CML Clinical Trials (Greater Than or Equal to 10% of All Patients in Any Trial)(1)
 | Myeloid blast Crisis (n = 260) |  | Accelerated phase (n = 235) |  | Chronic phase, IFN failure (n = 532)
 | % |  | % |  | %
Preferred term | All Grades | Grade 3/4 | All Grades | Grade 3/4 | All Grades | Grade 3/4
Fluid retention | 72 | 11 | 76 | 6 | 69 | 4
-Superficial edema | 66 | 6 | 74 | 3 | 67 | 2
-Other fluid retention reactions(2) | 22 | 6 | 15 | 4 | 7 | 2
Nausea | 71 | 5 | 73 | 5 | 63 | 3
Muscle cramps | 28 | 1 | 47 | 0.4 | 62 | 2
Vomiting | 54 | 4 | 58 | 3 | 36 | 2
Diarrhea | 43 | 4 | 57 | 5 | 48 | 3
Hemorrhage | 53 | 19 | 49 | 11 | 30 | 2
- CNS hemorrhage | 9 | 7 | 3 | 3 | 2 | 1
- GI hemorrhage | 8 | 4 | 6 | 5 | 2 | 0.4
Musculoskeletal pain | 42 | 9 | 49 | 9 | 38 | 2
Fatigue | 30 | 4 | 46 | 4 | 48 | 1
Skin rash | 36 | 5 | 47 | 5 | 47 | 3
Pyrexia | 41 | 7 | 41 | 8 | 21 | 2
Arthralgia | 25 | 5 | 34 | 6 | 40 | 1
Headache | 27 | 5 | 32 | 2 | 36 | 0.6
Abdominal pain | 30 | 6 | 33 | 4 | 32 | 1
Weight increased | 5 | 1 | 17 | 5 | 32 | 7
Cough | 14 | 0.8 | 27 | 0.9 | 20 | 0
Dyspepsia | 12 | 0 | 22 | 0 | 27 | 0
Myalgia | 9 | 0 | 24 | 2 | 27 | 0.2
Nasopharyngitis | 10 | 0 | 17 | 0 | 22 | 0.2
Asthenia | 18 | 5 | 21 | 5 | 15 | 0.2
Dyspnea | 15 | 4 | 21 | 7 | 12 | 0.9
Upper respiratory tract infection | 3 | 0 | 12 | 0.4 | 19 | 0
Anorexia | 14 | 2 | 17 | 2 | 7 | 0
Night sweats | 13 | 0.8 | 17 | 1 | 14 | 0.2
Constipation | 16 | 2 | 16 | 0.9 | 9 | 0.4
Dizziness | 12 | 0.4 | 13 | 0 | 16 | 0.2
Pharyngitis | 10 | 0 | 12 | 0 | 15 | 0
Insomnia | 10 | 0 | 14 | 0 | 14 | 0.2
Pruritus | 8 | 1 | 14 | 0.9 | 14 | 0.8
Hypokalemia | 13 | 4 | 9 | 2 | 6 | 0.8
Pneumonia | 13 | 7 | 10 | 7 | 4 | 1
Anxiety | 8 | 0.8 | 12 | 0 | 8 | 0.4
Liver toxicity | 10 | 5 | 12 | 6 | 6 | 3
Rigors | 10 | 0 | 12 | 0.4 | 10 | 0
Chest pain | 7 | 2 | 10 | 0.4 | 11 | 0.8
Influenza | 0.8 | 0.4 | 6 | 0 | 11 | 0.2
Sinusitis | 4 | 0.4 | 11 | 0.4 | 9 | 0.4
Abbreviations: CML, chronic myeloid leukemia; IFN, Interferon-alpha.
(1)All adverse reactions occurring in greater than or equal to 10% of patients are listed regardless of suspected relationship to treatment.
(2)Other fluid retention reactions include pleural effusion, ascites, pulmonary edema, pericardial effusion, anasarca, edema aggravated, and fluid retention not otherwise specified.

Hematologic and Biochemistry Laboratory Abnormalities

Cytopenias, and particularly neutropenia and thrombocytopenia, were a consistent finding in all studies, with a higher frequency at doses greater than or equal to 750 mg (Phase 1 study). The occurrence of cytopenias in CML patients was also dependent on the stage of the disease.

In patients with newly diagnosed CML, cytopenias were less frequent than in the other CML patients (see Tables 5, 6, and 7). The frequency of Grade 3 or 4 neutropenia and thrombocytopenia was between 2- and 3-fold higher in blast crisis and accelerated phase compared to chronic phase (see Tables 4 and 5). The median duration of the neutropenic and thrombocytopenic episodes varied from 2 to 3 weeks, and from 2 to 4 weeks, respectively.

These reactions can usually be managed with either a reduction of the dose or an interruption of treatment with Gleevec, but may require permanent discontinuation of treatment.

Table 5: Laboratory Abnormalities in Newly Diagnosed CML Clinical Trial (Gleevec Versus IFN+Ara-C)
 | Gleevec N = 551 |  | IFN+Ara−C N = 533
 | % |  | %
CTC Grades | Grade 3 | Grade 4 | Grade 3 | Grade 4
Hematology parameters*
− Neutropenia* | 13.1 | 3.6 | 20.8 | 4.5
− Thrombocytopenia* | 8.5 | 0.4 | 15.9 | 0.6
− Anemia | 3.3 | 1.1 | 4.1 | 0.2
Biochemistry parameters
− Elevated creatinine | 0 | 0 | 0.4 | 0
− Elevated bilirubin | 0.9 | 0.2 | 0.2 | 0
− Elevated alkaline phosphatase | 0.2 | 0 | 0.8 | 0
− Elevated SGOT (AST)/SGPT (ALT) | 4.7 | 0.5 | 7.1 | 0.4
Abbreviations: CML, chronic myeloid leukemia; IFN, Interferon-alpha; SGOT, serum glutamic-oxaloacetic transaminase is now referred to as aspartate aminotransferase (AST); SGPT, serum glutamic-pyruvic transaminase is now referred to as alanine aminotransferase (ALT).
*p less than 0.001 (difference in Grade 3 plus 4 abnormalities between the two treatment groups).

Table 6: Percent Incidence of Clinically Relevant Grade 3/4* Laboratory Abnormalities in the Newly Diagnosed CML Clinical Trial (Gleevec Versus Nilotinib)
 | Gleevec 400 mg once daily N = 280 (%) | Nilotinib 300 mg twice daily N = 279 (%)
Hematologic parameters
Thrombocytopenia | 9 | 10
Neutropenia | 22 | 12
Anemia | 6 | 4
Biochemistry parameters
Elevated lipase | 4 | 9
Hyperglycemia | < 1 | 7
Hypophosphatemia | 10 | 8
Elevated bilirubin (total) | < 1 | 4
Elevated SGPT (ALT) | 3 | 4
Hyperkalemia | 1 | 2
Hyponatremia | < 1 | 1
Hypokalemia | 2 | < 1
Elevated SGOT (AST) | 1 | 1
Decreased albumin | < 1 | 0
Hypocalcemia | < 1 | < 1
Elevated alkaline phosphatase | < 1 | 0
Elevated creatinine | < 1 | 0
Abbreviations: CML, chronic myeloid leukemia; SGOT, serum glutamic-oxaloacetic transaminase is now referred to as aspartate aminotransferase (AST); SGPT, serum glutamic-pyruvic transaminase is now referred to as alanine aminotransferase (ALT).
*NCI Common Terminology Criteria for Adverse Events, version 3.0.

Table 7: Laboratory Abnormalities in Other CML Clinical Trials
 | Myeloid blast crisis (n = 260) |  | Accelerated phase (n = 235) |  | Chronic phase, IFN failure (n = 532)
 | 600 mg n = 223 400 mg n = 37 |  | 600 mg n = 158 400 mg n = 77 |  | 400 mg
 | % |  | % |  | %
CTC Grades (1) | Grade 3 | Grade 4 | Grade 3 | Grade 4 | Grade 3 | Grade 4
Hematology parameters
− Neutropenia | 16 | 48 | 23 | 36 | 27 | 9
− Thrombocytopenia | 30 | 33 | 31 | 13 | 21 | < 1
− Anemia | 42 | 11 | 34 | 7 | 6 | 1
Biochemistry parameters
− Elevated creatinine | 1.5 | 0 | 1.3 | 0 | 0.2 | 0
− Elevated bilirubin | 3.8 | 0 | 2.1 | 0 | 0.6 | 0
− Elevated alkaline phosphatase | 4.6 | 0 | 5.5 | 0.4 | 0.2 | 0
− Elevated SGOT (AST) | 1.9 | 0 | 3.0 | 0 | 2.3 | 0
− Elevated SGPT (ALT) | 2.3 | 0.4 | 4.3 | 0 | 2.1 | 0
Abbreviations: CML, chronic myeloid leukemia; CTC, common terminology criteria; IFN, Interferon-alpha; SGOT, serum glutamic-oxaloacetic transaminase is now referred to as aspartate aminotransferase (AST); SGPT, serum glutamic-pyruvic transaminase is now referred to as alanine aminotransferase (ALT).
(1)CTC Grades: neutropenia (Grade 3 greater than or equal to 0.5–1.0 x 10^9/L, Grade 4 less than 0.5 x 10^9/L), thrombocytopenia (Grade 3 greater than or equal to 10–50 x 10^9/L, Grade 4 less than 10 x 10^9/L), anemia (hemoglobin greater than or equal to 65–80 g/L, Grade 4 less than 65 g/L), elevated creatinine (Grade 3 greater than 3–6 x upper limit normal range [ULN], Grade 4 greater than 6 x ULN), elevated bilirubin (Grade 3 greater than 3–10 x ULN, Grade 4 greater than 10 x ULN), elevated alkaline phosphatase (Grade 3 greater than 5–20 x ULN, Grade 4 greater than 20 x ULN), elevated SGOT or SGPT (Grade 3 greater than 5–20 x ULN, Grade 4 greater than 20 x ULN).

Hepatotoxicity

Severe elevation of transaminases or bilirubin occurred in approximately 5% of CML patients (see Tables 6 and 7) and were usually managed with dose reduction or interruption (the median duration of these episodes was approximately 1 week). Treatment was discontinued permanently because of liver laboratory abnormalities in less than 1.0% of CML patients. One patient, who was taking acetaminophen regularly for fever, died of acute liver failure. In the Phase 2 GIST trial, Grade 3 or 4 SGPT (ALT) elevations were observed in 6.8% of patients and Grade 3 or 4 SGOT (AST) elevations were observed in 4.8% of patients. Bilirubin elevation was observed in 2.7% of patients.

Adverse Reactions in Pediatric Population

Single-Agent Therapy

The overall safety profile of pediatric patients treated with Gleevec in 93 children studied was similar to that found in studies with adult patients, except that musculoskeletal pain was less frequent (20.5%) and peripheral edema was not reported. Nausea and vomiting were the most commonly reported individual adverse reactions with an incidence similar to that seen in adult patients. Most patients experienced adverse reactions at some time during the study. The incidence of Grade 3/4 events across all types of adverse reactions was 75%; the events with the highest Grade 3/4 incidence in CML pediatric patients were mainly related to myelosuppression.

In Combination with Multi-Agent Chemotherapy

Pediatric and young adult patients with very high risk ALL, defined as those with an expected 5 year event-free survival (EFS) less than 45%, were enrolled after induction therapy on a multicenter, non-randomized cooperative group pilot protocol. The study population included patients with a median age of 10 years (1 to 21 years), 61% of whom were male, 75% were white, 7% were black, and 6% were Asian/Pacific Islander. Patients with Ph+ ALL (n = 92) were assigned to receive Gleevec and treated in 5 successive cohorts. Gleevec exposure was systematically increased in successive cohorts by earlier introduction and more prolonged duration.

The safety of Gleevec given in combination with intensive chemotherapy was evaluated by comparing the incidence of Grade 3 and 4 adverse events, neutropenia (less than 750/mcL) and thrombocytopenia (less than 75,000/mcL) in the 92 patients with Ph+ ALL compared to 65 patients with Ph- ALL enrolled on the trial who did not receive Gleevec. The safety was also evaluated comparing the incidence of adverse events in cycles of therapy administered with or without Gleevec. The protocol included up to 18 cycles of therapy. Patients were exposed to a cumulative total of 1425 cycles of therapy, 778 with Gleevec, and 647 without Gleevec. The adverse events that were reported with a 5% or greater incidence in patients with Ph+ ALL compared to Ph- ALL or with a 1% or greater incidence in cycles of therapy that included Gleevec are presented in Table 8.

Table 8: Adverse Reactions Reported More Frequently in Patients Treated With Study Drug (Greater Than 5%) or in Cycles With Study Drug (Greater Than 1%)
Adverse event | Per patient incidence Ph+ ALL with gleevec N = 92 n (%) | Per patient incidence Ph- ALL no gleevec N = 65 n (%) | Per patient per cycle incidence with gleevec* N = 778 n (%) | Per patient per cycle incidence no gleevec** N = 647 n (%)
Grade 3 and 4 adverse events
Nausea and/or vomiting | 15 (16) | 6 (9) | 28 (4) | 8 (1)
Hypokalemia | 31 (34) | 16 (25) | 72 (9) | 32 (5)
Pneumonitis | 7 (8) | 1 (1) | 7 (1) | 1 (< 1)
Pleural effusion | 6 (7) | 0 | 6 (1) | 0
Abdominal pain | 8 (9) | 2 (3) | 9 (1) | 3 (< 1)
Anorexia | 10 (11) | 3 (5) | 19 (2) | 4 (1)
Hemorrhage | 11 (12) | 4 (6) | 17 (2) | 8 (1)
Hypoxia | 8 (9) | 2 (3) | 12 (2) | 2 (< 1)
Myalgia | 5 (5) | 0 | 4 (1) | 1 (< 1)
Stomatitis | 15 (16) | 8 (12) | 22 (3) | 14 (2)
Diarrhea | 8 (9) | 3 (5) | 12 (2) | 3 (< 1)
Rash/Skin disorder | 4 (4) | 0 | 5 (1) | 0
Infection | 49 (53) | 32 (49) | 131 (17) | 92 (14)
Hepatic (transaminase and/or bilirubin) | 52 (57) | 38 (58) | 172 (22) | 113 (17)
Hypotension | 10 (11) | 5 (8) | 16 (2) | 6 (1)
Myelosuppression
Neutropenia (< 750/mcL) | 92 (100) | 63 (97) | 556 (71) | 218 (34)
Thrombocytopenia (< 75,000/mcL) | 90 (92) | 63 (97) | 431 (55) | 329 (51)
Abbreviations: Ph+ ALL, Philadelphia chromosome positive acute lymphoblastic leukemia; Ph- ALL, Philadelphia chromosome negative acute lymphoblastic leukemia.
*Defined as the frequency of adverse events (AEs) per patient per treatment cycles that included Gleevec (includes patients with Ph+ ALL that received cycles with Gleevec).
**Defined as the frequency of AEs per patient per treatment cycles that did not include Gleevec (includes patients with Ph+ ALL that received cycles without Gleevec as well as all patients with Ph- ALL who did not receive Gleevec in any treatment cycle).

Adverse Reactions in Other Subpopulations

In older patients (greater than or equal to 65 years old), with the exception of edema, where it was more frequent, there was no evidence of an increase in the incidence or severity of adverse reactions. In women there was an increase in the frequency of neutropenia, as well as Grade 1/2 superficial edema, headache, nausea, rigors, vomiting, rash, and fatigue. No differences were seen that were related to race but the subsets were too small for proper evaluation.

Acute Lymphoblastic Leukemia

The adverse reactions were similar for Ph+ ALL as for Ph+ CML. The most frequently reported drug-related adverse reactions reported in the Ph+ ALL studies were mild nausea and vomiting, diarrhea, myalgia, muscle cramps, and rash. Superficial edema was a common finding in all studies and were described primarily as periorbital or lower limb edemas. These edemas were reported as Grade 3/4 events in 6.3% of the patients and may be managed with diuretics, other supportive measures, or in some patients by reducing the dose of Gleevec.

Myelodysplastic/Myeloproliferative Diseases

Adverse reactions, regardless of relationship to study drug, that were reported in at least 10% of the patients treated with Gleevec for MDS/MPD in the Phase 2 study, are shown in Table 9.

Table 9: Adverse Reactions Regardless of Relationship to Study Drug Reported (More Than One Patient) in MPD Patients in the Phase 2 Study (Greater Than or Equal to 10% All Patients) All Grades
Preferred term | N = 7 n (%)
Nausea | 4 (57.1)
Diarrhea | 3 (42.9)
Anemia | 2 (28.6)
Fatigue | 2 (28.6)
Muscle cramp | 3 (42.9)
Arthralgia | 2 (28.6)
Periorbital edema | 2 (28.6)
Abbreviation: MPD, myeloproliferative disease.

Aggressive Systemic Mastocytosis

All aggressive systemic mastocytosis (ASM) patients experienced at least one adverse reaction at some time. The most frequently reported adverse reactions were diarrhea, nausea, ascites, muscle cramps, dyspnea, fatigue, peripheral edema, anemia, pruritus, rash, and lower respiratory tract infection. None of the 5 patients in the Phase 2 study with ASM discontinued Gleevec due to drug-related adverse reactions or abnormal laboratory values.

Hypereosinophilic Syndrome and Chronic Eosinophilic Leukemia

The safety profile in the HES/CEL patient population does not appear to be different from the safety profile of Gleevec observed in other hematologic malignancy populations, such as Ph+ CML. All patients experienced at least one adverse reaction, the most common being GI, cutaneous and musculoskeletal disorders. Hematological abnormalities were also frequent, with instances of CTC Grade 3 leukopenia, neutropenia, lymphopenia, and anemia.

Dermatofibrosarcoma Protuberans

Adverse reactions, regardless of relationship to study drug, that were reported in at least 10% of the 12 patients treated with Gleevec for DFSP in the Phase 2 study are shown in Table 10.

Table 10: Adverse Reactions Regardless of Relationship to Study Drug Reported in DFSP Patients in the Phase 2 Study (Greater Than or Equal to 10% All Patients) All Grades
Preferred term | N = 12 n (%)
Nausea | 5 (41.7)
Diarrhea | 3 (25.0)
Vomiting | 3 (25.0)
Periorbital edema | 4 (33.3)
Face edema | 2 (16.7)
Rash | 3 (25.0)
Fatigue | 5 (41.7)
Peripheral edema | 4 (33.3)
Pyrexia | 2 (16.7)
Eye edema | 4 (33.3)
Lacrimation increased | 3 (25.0)
Dyspnea exertional | 2 (16.7)
Anemia | 3 (25.0)
Rhinitis | 2 (16.7)
Anorexia | 2 (16.7)
Abbreviation: DFSP, dermatofibrosarcoma protuberans.

Clinically relevant or severe laboratory abnormalities in the 12 patients treated with Gleevec for DFSP in the Phase 2 study are presented in Table 11.

Table 11: Laboratory Abnormalities Reported in DFSP Patients in the Phase 2 Study
 | N = 12
CTC Grades (1) | Grade 3 % | Grade 4 %
Hematology parameters
- Anemia | 17 | 0
- Thrombocytopenia | 17 | 0
- Neutropenia | 0 | 8
Biochemistry parameters
- Elevated creatinine | 0 | 8
Abbreviation: CTC, common terminology criteria.
(1)CTC Grades: neutropenia (Grade 3 greater than or equal to 0.5–1.0 x 10^9/L, Grade 4 less than 0.5 x 10^9/L), thrombocytopenia (Grade 3 greater than or equal to 10–50 x 10^9/L, Grade 4 less than 10 x 10^9/L), anemia (Grade 3 greater than or equal to 65–80 g/L, Grade 4 less than 65 g/L), elevated creatinine (Grade 3 greater than 3–6 x upper limit normal range [ULN], Grade 4 greater than 6 x ULN).

Gastrointestinal Stromal Tumors

Unresectable and/or Malignant Metastatic GIST

In the Phase 3 trials, the majority of Gleevec-treated patients experienced adverse reactions at some time. The most frequently reported adverse reactions were edema, fatigue, nausea, abdominal pain, diarrhea, rash, vomiting, myalgia, anemia, and anorexia. Drug was discontinued for adverse reactions in a total of 89 patients (5.4%). Superficial edema, most frequently periorbital or lower extremity edema was managed with diuretics, other supportive measures, or by reducing the dose of Gleevec [see Dosage and Administration (2.13)]. Severe (CTC Grade 3/4) edema was observed in 182 patients (11.1%).

Adverse reactions, regardless of relationship to study drug, that were reported in at least 10% of the patients treated with Gleevec are shown in Table 12.

Overall the incidence of all grades of adverse reactions and the incidence of severe adverse reactions (CTC Grade 3 and above) were similar between the two treatment arms except for edema, which was reported more frequently in the 800 mg group.

Table 12: Number (%) of Patients With Adverse Reactions Regardless of Relationship to Study Drug Where Frequency is Greater Than or Equal to 10% in any One Group (Full Analysis Set) in the Phase 3 Unresectable and/or Malignant Metastatic GIST Clinical Trials
Reported or specified term | Imatinib 400 mg N = 818 |  | Imatinib 800 mg N = 822
 | All Grades % | Grades 3/4/5 % | All Grades % | Grades 3/4/5 %
Edema | 76.7 | 9.0 | 86.1 | 13.1
Fatigue/lethargy, malaise, asthenia | 69.3 | 11.7 | 74.9 | 12.2
Nausea | 58.1 | 9.0 | 64.5 | 7.8
Abdominal pain/cramping | 57.2 | 13.8 | 55.2 | 11.8
Diarrhea | 56.2 | 8.1 | 58.2 | 8.6
Rash/desquamation | 38.1 | 7.6 | 49.8 | 8.9
Vomiting | 37.4 | 9.2 | 40.6 | 7.5
Myalgia | 32.2 | 5.6 | 30.2 | 3.8
Anemia | 32.0 | 4.9 | 34.8 | 6.4
Anorexia | 31.1 | 6.6 | 35.8 | 4.7
Other GI toxicity | 25.2 | 8.1 | 28.1 | 6.6
Headache | 22.0 | 5.7 | 19.7 | 3.6
Other pain (excluding tumor related pain) | 20.4 | 5.9 | 20.8 | 5.0
Other dermatology/skin toxicity | 17.6 | 5.9 | 20.1 | 5.7
Leukopenia | 17.0 | 0.7 | 19.6 | 1.6
Other constitutional symptoms | 16.7 | 6.4 | 15.2 | 4.4
Cough | 16.1 | 4.5 | 14.5 | 3.2
Infection (without neutropenia) | 15.5 | 6.6 | 16.5 | 5.6
Pruritus | 15.4 | 5.4 | 18.9 | 4.3
Other neurological toxicity | 15.0 | 6.4 | 15.2 | 4.9
Constipation | 14.8 | 5.1 | 14.4 | 4.1
Other renal/genitourinary toxicity | 14.2 | 6.5 | 13.6 | 5.2
Arthralgia (joint pain) | 13.6 | 4.8 | 12.3 | 3.0
Dyspnea (shortness of breath) | 13.6 | 6.8 | 14.2 | 5.6
Fever in absence of neutropenia (ANC < 1.0 x 10^9/L) | 13.2 | 4.9 | 12.9 | 3.4
Sweating | 12.7 | 4.6 | 8.5 | 2.8
Other hemorrhage | 12.3 | 6.7 | 13.3 | 6.1
Weight gain | 12.0 | 1.0 | 10.6 | 0.6
Alopecia | 11.9 | 4.3 | 14.8 | 3.2
Dyspepsia/heartburn | 11.5 | 0.6 | 10.9 | 0.5
Neutropenia/granulocytopenia | 11.5 | 3.1 | 16.1 | 4.1
Rigors/chills | 11.0 | 4.6 | 10.2 | 3.0
Dizziness/lightheadedness | 11.0 | 4.8 | 10.0 | 2.8
Creatinine increase | 10.8 | 0.4 | 10.1 | 0.6
Flatulence | 10.0 | 0.2 | 10.1 | 0.1
Stomatitis/pharyngitis (oral/pharyngeal mucositis) | 9.2 | 5.4 | 10.0 | 4.3
Lymphopenia | 6.0 | 0.7 | 10.1 | 1.9
Abbreviations: ANC, absolute neutrophil count; GI, gastrointestinal; GIST, gastrointestinal stromal tumors.

Clinically relevant or severe abnormalities of routine hematologic or biochemistry laboratory values were not reported or evaluated in the Phase 3 GIST trials. Severe abnormal laboratory values reported in the Phase 2 GIST trial are presented in Table 13.

Table 13: Laboratory Abnormalities in the Phase 2 Unresectable and/or Malignant Metastatic GIST Trial
 | 400 mg (n = 73) |  | 600 mg (n = 74)
 | % |  | %
CTC Grades^1 | Grade 3 | Grade 4 | Grade 3 | Grade 4
Hematology parameters
− Anemia | 3 | 0 | 8 | 1
− Thrombocytopenia | 0 | 0 | 1 | 0
− Neutropenia | 7 | 3 | 8 | 3
Biochemistry parameters
− Elevated creatinine | 0 | 0 | 3 | 0
− Reduced albumin | 3 | 0 | 4 | 0
− Elevated bilirubin | 1 | 0 | 1 | 3
− Elevated alkaline phosphatase | 0 | 0 | 3 | 0
− Elevated SGOT (AST) | 4 | 0 | 3 | 3
− Elevated SGPT (ALT) | 6 | 0 | 7 | 1
Abbreviations: CTC, common terminology criteria; GIST, gastrointestinal stromal tumors; SGOT, serum glutamic-oxaloacetic transaminase is now referred to as aspartate aminotransferase (AST); SGPT, serum glutamic-pyruvic transaminase is now referred to as alanine aminotransferase (ALT).
^1CTC Grades: neutropenia (Grade 3 greater than or equal to 0.5–1.0 x 10^9/L, Grade 4 less than 0.5 x 10^9/L), thrombocytopenia (Grade 3 greater than or equal to 10–50 x 10^9/L, Grade 4 less than 10 x 10^9/L), anemia (Grade 3 greater than or equal to 65–80 g/L, Grade 4 less than 65 g/L), elevated creatinine (Grade 3 greater than 3–6 x upper limit normal range [ULN], Grade 4 greater than 6 x ULN), elevated bilirubin (Grade 3 greater than 3–10 x ULN, Grade 4 greater than 10 x ULN), elevated alkaline phosphatase, SGOT or SGPT (Grade 3 greater than 5–20 x ULN, Grade 4 greater than 20 x ULN), albumin (Grade 3 less than 20 g/L).

Adjuvant Treatment of GIST

In Study 1, the majority of both Gleevec and placebo-treated patients experienced at least one adverse reaction at some time. The most frequently reported adverse reactions were similar to those reported in other clinical studies in other patient populations and include diarrhea, fatigue, nausea, edema, decreased hemoglobin, rash, vomiting, and abdominal pain. No new adverse reactions were reported in the adjuvant GIST-treatment setting that had not been previously reported in other patient populations, including patients with unresectable and/or malignant metastatic GIST. Drug was discontinued for adverse reactions in 57 patients (17%) and 11 patients (3%) of the Gleevec and placebo-treated patients, respectively. Edema, GI disturbances (nausea, vomiting, abdominal distention, and diarrhea), fatigue, low hemoglobin, and rash were the most frequently reported adverse reactions at the time of discontinuation.

In Study 2, discontinuation of therapy due to adverse reactions occurred in 15 patients (8%) and 27 patients (14%) of the Gleevec 12-month, and 36-month treatment arms, respectively. As in previous trials the most common adverse reactions were diarrhea, fatigue, nausea, edema, decreased hemoglobin, rash, vomiting, and abdominal pain.

Adverse reactions, regardless of relationship to study drug, that were reported in at least 5% of the patients treated with Gleevec are shown in Table 14 (Study 1) and Table 15 (Study 2). There were no deaths attributable to Gleevec treatment in either trial.

Table 14: Adverse Reactions Regardless of Relationship to Study Drug Reported in Study 1 (Greater Than or Equal to 5% of Gleevec-Treated Patients)(1)
 | All CTC Grades |  | CTC Grade 3* and Above
 | Gleevec (n = 337) | Placebo (n = 345) | Gleevec (n = 337) | Placebo (n = 345)
Preferred term | % | % | % | %
Diarrhea | 59.3 | 29.3 | 3.0 | 1.4
Fatigue | 57.0 | 40.9 | 2.1 | 1.2
Nausea | 53.1 | 27.8 | 2.4 | 1.2
Periorbital edema | 47.2 | 14.5 | 1.2 | 0
Hemoglobin decreased | 46.9 | 27.0 | 0.6 | 0
Peripheral edema | 26.7 | 14.8 | 0.3 | 0
Rash (Exfoliative) | 26.1 | 12.8 | 2.7 | 0
Vomiting | 25.5 | 13.9 | 2.4 | 0.6
Abdominal pain | 21.1 | 22.3 | 3.0 | 1.4
Headache | 19.3 | 20.3 | 0.6 | 0
Dyspepsia | 17.2 | 13.0 | 0.9 | 0
Anorexia | 16.9 | 8.7 | 0.3 | 0
Weight increased | 16.9 | 11.6 | 0.3 | 0
Liver enzymes (ALT) increased | 16.6 | 13.0 | 2.7 | 0
Muscle spasms | 16.3 | 3.3 | 0 | 0
Neutrophil count decreased | 16.0 | 6.1 | 3.3 | 0.9
Arthralgia | 15.1 | 14.5 | 0 | 0.3
White blood cell count decreased | 14.5 | 4.3 | 0.6 | 0.3
Constipation | 12.8 | 17.7 | 0 | 0.3
Dizziness | 12.5 | 10.7 | 0 | 0.3
Liver enzymes (AST) increased | 12.2 | 7.5 | 2.1 | 0
Myalgia | 12.2 | 11.6 | 0 | 0.3
Blood creatinine increased | 11.6 | 5.8 | 0 | 0.3
Cough | 11.0 | 11.3 | 0 | 0
Pruritus | 11.0 | 7.8 | 0.9 | 0
Weight decreased | 10.1 | 5.2 | 0 | 0
Hyperglycemia | 9.8 | 11.3 | 0.6 | 1.7
Insomnia | 9.8 | 7.2 | 0.9 | 0
Lacrimation increased | 9.8 | 3.8 | 0 | 0
Alopecia | 9.5 | 6.7 | 0 | 0
Flatulence | 8.9 | 9.6 | 0 | 0
Rash | 8.9 | 5.2 | 0.9 | 0
Abdominal distension | 7.4 | 6.4 | 0.3 | 0.3
Back pain | 7.4 | 8.1 | 0.6 | 0
Pain in extremity | 7.4 | 7.2 | 0.3 | 0
Hypokalemia | 7.1 | 2.0 | 0.9 | 0.6
Depression | 6.8 | 6.4 | 0.9 | 0.6
Facial edema | 6.8 | 1.2 | 0.3 | 0
Blood alkaline phosphatase increased | 6.5 | 7.5 | 0 | 0
Dry skin | 6.5 | 5.2 | 0 | 0
Dysgeusia | 6.5 | 2.9 | 0 | 0
Abdominal pain upper | 6.2 | 6.4 | 0.3 | 0
Neuropathy peripheral | 5.9 | 6.4 | 0 | 0
Hypocalcemia | 5.6 | 1.7 | 0.3 | 0
Leukopenia | 5.0 | 2.6 | 0.3 | 0
Platelet count decreased | 5.0 | 3.5 | 0 | 0
Stomatitis | 5.0 | 1.7 | 0.6 | 0
Upper respiratory tract infection | 5.0 | 3.5 | 0 | 0
Vision blurred | 5.0 | 2.3 | 0 | 0
Abbreviations: CTC, common terminology criteria; GIST, gastrointestinal stromal tumors; SGOT, serum glutamic-oxaloacetic transaminase is now referred to as aspartate aminotransferase (AST); SGPT, serum glutamic-pyruvic transaminase is now referred to as alanine aminotransferase (ALT).
*NCI Common Terminology Criteria for Adverse Events, version 3.0.
(1)All adverse reactions occurring in greater than or equal to 5% of patients are listed regardless of suspected relationship to treatment.
A patient with multiple occurrences of an adverse reaction is counted only once in the adverse reaction category.

Table 15: Adverse Reactions Regardless of Relationship to Study Drug by Preferred Term All Grades and 3/4 Grades (Greater Than or Equal to 5% of Gleevec-Treated Patients) Study 2(1)
Preferred term | All CTC Grades |  | CTC Grades 3 and above
 | Gleevec 12 Months (N = 194) % | Gleevec 36 Months (N = 198) % | Gleevec 12 Months (N = 194) % | Gleevec 36 Months (N = 198) %
Patients with at least one AE | 99.0 | 100.0 | 20.1 | 32.8
Hemoglobin decreased | 72.2 | 80.3 | 0.5 | 0.5
Periorbital edema | 59.3 | 74.2 | 0.5 | 1.0
Blood lactate dehydrogenase increased | 43.3 | 60.1 | 0 | 0
Diarrhea | 43.8 | 54.0 | 0.5 | 2.0
Nausea | 44.8 | 51.0 | 1.5 | 0.5
Muscle spasms | 30.9 | 49.0 | 0.5 | 1.0
Fatigue | 48.5 | 48.5 | 1.0 | 0.5
White blood cell count decreased | 34.5 | 47.0 | 2.1 | 3.0
Pain | 25.8 | 45.5 | 1.0 | 3.0
Blood creatinine increased | 30.4 | 44.4 | 0 | 0
Peripheral edema | 33.0 | 40.9 | 0.5 | 1.0
Dermatitis | 29.4 | 38.9 | 2.1 | 1.5
Aspartate aminotransferase increased | 30.9 | 37.9 | 1.5 | 3.0
Alanine aminotransferase increased | 28.9 | 34.3 | 2.1 | 3.0
Neutrophil count decreased | 24.2 | 33.3 | 4.6 | 5.1
Hypoproteinemia | 23.7 | 31.8 | 0 | 0
Infection | 13.9 | 27.8 | 1.5 | 2.5
Weight increased | 13.4 | 26.8 | 0 | 0.5
Pruritus | 12.9 | 25.8 | 0 | 0
Flatulence | 19.1 | 24.7 | 1.0 | 0.5
Vomiting | 10.8 | 22.2 | 0.5 | 1.0
Dyspepsia | 17.5 | 21.7 | 0.5 | 1.0
Hypoalbuminemia | 11.9 | 21.2 | 0 | 0
Edema | 10.8 | 19.7 | 0 | 0.5
Abdominal distension | 11.9 | 19.2 | 0.5 | 0
Headache | 8.2 | 18.2 | 0 | 0
Lacrimation increased | 18.0 | 17.7 | 0 | 0
Arthralgia | 8.8 | 17.2 | 0 | 1.0
Blood alkaline phosphatase increased | 10.8 | 16.7 | 0 | 0.5
Dyspnea | 6.2 | 16.2 | 0.5 | 1.5
Myalgia | 9.3 | 15.2 | 0 | 1.0
Platelet count decreased | 11.3 | 14.1 | 0 | 0
Blood bilirubin increased | 11.3 | 13.1 | 0 | 0
Dysgeusia | 9.3 | 12.6 | 0 | 0
Paresthesia | 5.2 | 12.1 | 0 | 0.5
Vision blurred | 10.8 | 11.1 | 1.0 | 0.5
Alopecia | 11.3 | 10.6 | 0 | 0
Decreased appetite | 9.8 | 10.1 | 0 | 0
Constipation | 8.8 | 9.6 | 0 | 0
Pyrexia | 6.2 | 9.6 | 0 | 0
Depression | 3.1 | 8.1 | 0 | 0
Abdominal pain | 2.6 | 7.6 | 0 | 0
Conjunctivitis | 5.2 | 7.6 | 0 | 0
Photosensitivity reaction | 3.6 | 7.1 | 0 | 0
Dizziness | 4.6 | 6.6 | 0.5 | 0
Hemorrhage | 3.1 | 6.6 | 0 | 0
Dry skin | 6.7 | 6.1 | 0.5 | 0
Nasopharyngitis | 1.0 | 6.1 | 0 | 0.5
Palpitations | 5.2 | 5.1 | 0 | 0
Abbreviations: AE, adverse event; CTC, common terminology criteria.
(1)All adverse reactions occurring in greater than or equal to 5% of patients are listed regardless of suspected relationship to treatment.
A patient with multiple occurrences of an adverse reaction is counted only once in the adverse reaction category.

Adverse Reactions from Multiple Clinical Trials

Cardiac Disorders:

Estimated 1%-10%: palpitations, pericardial effusion

Estimated 0.1%-1%: congestive cardiac failure, tachycardia, pulmonary edema

Estimated 0.01%-0.1%: arrhythmia, atrial fibrillation, cardiac arrest, myocardial infarction, angina pectoris

Vascular Disorders:

Estimated 1%-10%: flushing, hemorrhage

Estimated 0.1%-1%: hypertension, hypotension, peripheral coldness, Raynaud’s phenomenon, hematoma, subdural hematoma

Investigations:

Estimated 1%-10%: blood creatine phosphokinase (CPK) increased, blood amylase increased

Estimated 0.1%-1%: blood lactate dehydrogenase (LDH) increased

Skin and Subcutaneous Tissue Disorders:

Estimated 1%-10%: dry skin, alopecia, face edema, erythema, photosensitivity reaction, nail disorder, purpura

Estimated 0.1%-1%: exfoliative dermatitis, bullous eruption, psoriasis, rash pustular, contusion, sweating increased, urticaria, ecchymosis, increased tendency to bruise, hypotrichosis, skin hypopigmentation, skin hyperpigmentation, onychoclasis, folliculitis, petechiae, erythema multiforme, panniculitis (including erythema nodosum)

Estimated 0.01%-0.1%: vesicular rash, Stevens-Johnson syndrome, acute generalized exanthematous pustulosis, acute febrile neutrophilic dermatosis (Sweet’s syndrome), nail discoloration, angioneurotic edema, leucocytoclastic vasculitis

Gastrointestinal Disorders:

Estimated 1%-10%: abdominal distention, gastroesophageal reflux, dry mouth, gastritis

Estimated 0.1%-1%: gastric ulcer, stomatitis, mouth ulceration, eructation, melena, esophagitis, ascites, hematemesis, chelitis, dysphagia, pancreatitis

Estimated 0.01%-0.1%: colitis, ileus, inflammatory bowel disease

General Disorders and Administration-Site Conditions:

Estimated 1%-10%: weakness, anasarca, chills

Estimated 0.1%-1%: malaise

Blood and Lymphatic System Disorders:

Estimated 1%-10%: pancytopenia, febrile neutropenia, lymphopenia, eosinophilia

Estimated 0.1%-1%: thrombocythemia, bone marrow depression, lymphadenopathy

Estimated 0.01%-0.1%: hemolytic anemia, aplastic anemia

Hepatobiliary Disorders:

Estimated 0.1%-1%: hepatitis, jaundice

Estimated 0.01%-0.1%: hepatic failure and hepatic necrosis^1

Immune System Disorders:

Estimated 0.01%-0.1%: angioedema

Infections and Infestations:

Estimated 0.1%-1%: sepsis, herpes simplex, herpes zoster, cellulitis, urinary tract infection, gastroenteritis

Estimated 0.01%-0.1%: fungal infection

Metabolism and Nutrition Disorders:

Estimated 1%-10%: weight decreased, decreased appetite

Estimated 0.1%-1%: dehydration, gout, increased appetite, hyperuricemia, hypercalcemia, hyperglycemia, hyponatremia, hyperkalemia, hypomagnesemia

Musculoskeletal and Connective Tissue Disorders:

Estimated 1%-10%: joint swelling

Estimated 0.1%-1%: joint and muscle stiffness, muscular weakness, arthritis

Nervous System/Psychiatric Disorders:

Estimated 1%-10%: paresthesia, hypesthesia

Estimated 0.1%-1%: syncope, peripheral neuropathy, somnolence, migraine, memory impairment, libido decreased, sciatica, restless leg syndrome, tremor

Estimated 0.01%-0.1%: increased intracranial pressure^1, confusional state, convulsions, optic neuritis

Renal and Urinary Disorders:

Estimated 0.1%-1%: renal failure acute, urinary frequency increased, hematuria, renal pain

Reproductive System and Breast Disorders:

Estimated 0.1%-1%: breast enlargement, menorrhagia, sexual dysfunction, gynecomastia, erectile dysfunction, menstruation irregular, nipple pain, scrotal edema

Respiratory, Thoracic and Mediastinal Disorders:

Estimated 1%-10%: epistaxis

Estimated 0.1%-1%: pleural effusion

Estimated 0.01%-0.1%: interstitial pneumonitis, pulmonary fibrosis, pleuritic pain, pulmonary hypertension, pulmonary hemorrhage

Endocrine Disorders:

Estimated 0.1%-1%: hypothyroidism, hyperthyroidism

Eye, Ear, and Labyrinth Disorders:

Estimated 1%-10%: conjunctivitis, vision blurred, orbital edema, conjunctival hemorrhage, dry eye

Estimated 0.1%-1%: vertigo, tinnitus, eye irritation, eye pain, scleral hemorrhage, retinal hemorrhage, blepharitis, macular edema, hearing loss, cataract

Estimated 0.01%-0.1%: papilledema^1, glaucoma

^1Including some fatalities.

6.2 Postmarketing Experience

The following additional adverse reactions have been identified during post approval use of Gleevec. Because these reactions are reported voluntarily from a population of uncertain size, it is not always possible to reliably estimate their frequency or establish a causal relationship to drug exposure.

Blood and Lymphatic System Disorders: thrombotic microangiopathy

Cardiac Disorders: pericarditis, cardiac tamponade^1

Eye Disorders: vitreous hemorrhage

Gastrointestinal Disorders: ileus/intestinal obstruction, tumor hemorrhage/tumor necrosis, GI perforation^1 [see Warnings and Precautions (5.6)], diverticulitis, gastric antral vascular ectasia

Infections: hepatitis B virus reactivation^1

Musculoskeletal and Connective Tissue Disorders: osteonecrosis, rhabdomyolysis/myopathy, growth retardation in children, musculoskeletal pain upon treatment discontinuation (including myalgia, pain in extremity, arthalgia, bone pain)

Nervous System Disorders: cerebral edema^1

Reproduction Disorders: hemorrhagic corpus luteum/hemorrhagic ovarian cyst

Respiratory, Thoracic and Mediastinal Disorders: acute respiratory failure^1, interstitial lung disease

Skin and Subcutaneous Tissue Disorders: lichenoid keratosis, lichen planus, toxic epidermal necrolysis, palmar-plantar erythrodysesthesia syndrome, drug rash with eosinophilia and systemic symptoms (DRESS), pseudoporphyria, pemphigus

Vascular Disorders: thrombosis/embolism, anaphylactic shock

^1Including some fatalities.

7 DRUG INTERACTIONS

7.1 Agents Inducing CYP3A Metabolism

Concomitant administration of Gleevec and strong CYP3A4 inducers may reduce total exposure of imatinib; consider alternative agents [see Clinical Pharmacology (12.3)].

7.2 Agents Inhibiting CYP3A Metabolism

Concomitant administration of Gleevec and strong CYP3A4 inhibitors may result in a significant imatinib exposure increase. Grapefruit juice may also increase plasma concentrations of imatinib; avoid grapefruit juice [see Clinical Pharmacology (12.3)].

7.3 Interactions With Drugs Metabolized by CYP3A4

Gleevec will increase plasma concentration of CYP3A4 metabolized drugs (e.g., triazolo-benzodiazepines, dihydropyridine calcium channel blockers, certain HMG-CoA reductase inhibitors, etc.). Use caution when administering Gleevec with CYP3A4 substrates that have a narrow therapeutic window.

Because warfarin is metabolized by CYP2C9 and CYP3A4, use low-molecular weight or standard heparin instead of warfarin in patients who require anticoagulation [see Clinical Pharmacology (12.3)].

7.4 Interactions With Drugs Metabolized by CYP2D6

Use caution when administering Gleevec with CYP2D6 substrates that have a narrow therapeutic window.

7.5 Interactions With Methotrexate

Gleevec may delay the clearance of methotrexate and result in sustained methotrexate concentrations when methotrexate is used at high doses (> 500 mg/m^2). Refer to the prescribing information for methotrexate injection for recommendations on management of methotrexate concentrations.

8 USE IN SPECIFIC POPULATIONS

8.1 Pregnancy

Risk Summary

Gleevec can cause fetal harm when administered to a pregnant woman based on human and animal data. There are no clinical studies regarding use of Gleevec in pregnant women. There have been postmarket reports of spontaneous abortions and congenital anomalies from women who have been exposed to Gleevec during pregnancy. Reproductive studies in rats have demonstrated that imatinib mesylate induced teratogenicity and increased incidence of congenital abnormalities following prenatal exposure to imatinib mesylate at doses equal to the highest recommended human dose of 800 mg/day based on BSA. Advise women to avoid pregnancy when taking Gleevec. If this drug is used during pregnancy, or if the patient becomes pregnant while taking this drug, apprise the patient of the potential hazard to the fetus.

The background risk of major birth defects and miscarriage for the indicated population is not known; however, in the U.S. general population, the estimated background risk of major birth defects of clinically recognized pregnancies is 2% to 4% and of miscarriage is 15% to 20%.

Data

Animal Data

In embryo-fetal development studies in rats and rabbits, pregnant animals received oral doses of imatinib mesylate up to 100 mg/kg/day and 60 mg/kg/day, respectively, during the period of organogenesis.

In rats, imatinib mesylate was teratogenic at 100 mg/kg/day (approximately equal to the maximum human dose of 800 mg/day based on BSA), the number of fetuses with encephalocoele and exencephaly was higher than historical control values and these findings were associated with missing or underdeveloped cranial bones. Lower mean fetal body weights were associated with retarded skeletal ossifications.

In rabbits, at doses 1.5 times higher than the maximum human dose of 800 mg/day based on BSA, no effects on the reproductive parameters with respect to implantation sites, number of live fetuses, sex ratio or fetal weight were observed. The examinations of the fetuses did not reveal any drug related morphological changes.

In a pre- and postnatal development study in rats, pregnant rats received oral doses of imatinib mesylate during gestation (organogenesis) and lactation up to 45 mg/kg/day. Five animals developed a red vaginal discharge in the 45 mg/kg/day group on Days 14 or 15 of gestation, the significance of which is unknown since all females produced viable litters and none had increased post-implantation loss. Other maternal effects noted only at the dose of 45 mg/kg/day (approximately one-half the maximum human dose of 800 mg/day based on BSA) included an increased number of stillborn pups and pups dying between postpartum Days 0 and 4. In the F1 offspring at this same dose level, mean body weights were reduced from birth until terminal sacrifice and the number of litters achieving criterion for preputial separation was slightly decreased. There were no other significant effects in developmental parameters or behavioral testing. F1 fertility was not affected but reproductive effects were noted at 45 mg/kg/day, including an increased number of resorptions and a decreased number of viable fetuses. The no-observed-effect level (NOEL) for both maternal animals and the F1 generation was 15 mg/kg/day.

8.2 Lactation

Risk Summary

Imatinib and its active metabolite are excreted into human milk. Because of the potential for serious adverse reactions in breastfed infants from Gleevec, advise a lactating woman not to breastfeed during treatment and for 1 month after the last dose.

Human Data

Based on data from 3 breastfeeding women taking Gleevec, the milk:plasma ratio is about 0.5 for imatinib and about 0.9 for the active metabolite. Considering the combined concentration of imatinib and active metabolite, a breastfed infant could receive up to 10% of the maternal therapeutic dose based on body weight.

8.3 Females and Males of Reproductive Potential

Human postmarketing reports and animal studies have shown Gleevec to be harmful to the developing fetus [see Use in Specific Populations (8.1)].

Pregnancy Testing

Test pregnancy status in females with reproductive potential prior to the initiation of treatment with Gleevec.

Contraception

Females

Advise female patients of reproductive potential to use effective contraception (methods that result in less than 1% pregnancy rates) when using Gleevec during treatment and for fourteen days after stopping treatment with Gleevec [see Use in Specific Populations (8.1)].

Infertility

The risk of infertility in females or males of reproductive potential has not been studied in humans. In a rat study, the fertility in males and females was not affected [see Nonclinical Toxicology (13)].

8.4 Pediatric Use

The safety and effectiveness of Gleevec have been demonstrated in pediatric patients with newly diagnosed Ph+ chronic phase CML and Ph+ ALL [see Clinical Studies (14.2, 14.4)]. There are no data in children under 1 year of age.

8.5 Geriatric Use

In the CML clinical studies, approximately 20% of patients were older than 65 years. In the study of patients with newly diagnosed CML, 6% of patients were older than 65 years. The frequency of edema was higher in patients older than 65 years as compared to younger patients; no other difference in the safety profile was observed [see Warnings and Precautions (5.1)]. The efficacy of Gleevec was similar in older and younger patients.

In the unresectable or metastatic GIST study, 16% of patients were older than 65 years. No obvious differences in the safety or efficacy profile were noted in patients older than 65 years as compared to younger patients, but the small number of patients does not allow a formal analysis.

In the adjuvant GIST study, 221 patients (31%) were older than 65 years. No difference was observed in the safety profile in patients older than 65 years as compared to younger patients, with the exception of a higher frequency of edema. The efficacy of Gleevec was similar in patients older than 65 years and younger patients.

8.6 Hepatic Impairment

The effect of hepatic impairment on the pharmacokinetics of both imatinib and its major metabolite, CGP74588, was assessed in 84 patients with cancer with varying degrees of hepatic impairment at imatinib doses ranging from 100 mg to 800 mg.

Mild and moderate hepatic impairment do not influence exposure to imatinib and CGP74588. In patients with severe hepatic impairment, the imatinib Cmax and area under curve (AUC) increased by 63% and 45% and the CGP74588 Cmax and AUC increased by 56% and 55%, relative to patients with normal hepatic function [see Clinical Pharmacology (12.3)]. Reduce the dose by 25% for patients with severe hepatic impairment [see Dosage and Administration (2.12)].

Table 16: Liver Function Classification
Liver function test | Normal (n = 14) | Mild (n = 30) | Moderate (n = 20) | Severe (n = 20)
Total bilirubin | less than or equal to ULN | greater than 1.0–1.5 times the ULN | greater than 1.5–3 times the ULN | greater than 3–10 times the ULN
SGOT | less than or equal to ULN | greater than ULN (can be normal if Total Bilirubin is greater than ULN) | Any | Any
Abbreviation: SGOT, serum glutamic-oxaloacetic transaminase is now referred to as aspartate aminotransferase (AST); ULN, upper limit of normal for the institution.

8.7 Renal Impairment

The effect of renal impairment on the pharmacokinetics of imatinib was assessed in 59 patients with cancer and varying degrees of renal impairment at single and steady state imatinib doses ranging from 100 to 800 mg/day. The mean exposure to imatinib (dose normalized AUC) in patients with mild and moderate renal impairment increased 1.5- to 2-fold compared to patients with normal renal function. There are not sufficient data in patients with severe renal impairment [see Clinical Pharmacology (12.3)]. Dose reductions are necessary for patients with moderate and severe renal impairment [see Dosage and Administration (2.12)].

Table 17: Renal Function Classification
Renal dysfunction | Renal function tests
Mild | CrCL = 40-59 mL/min
Moderate | CrCL = 20-39 mL/min
Severe | CrCL = less than 20 mL/min
Abbreviation: CrCL, creatinine clearance.

10 OVERDOSAGE

Experience with doses greater than 800 mg is limited. Isolated cases of Gleevec overdose have been reported. In the event of overdosage, observe the patient and give appropriate supportive treatment.

Adult Overdose

1,200 to 1,600 mg (duration varying between 1 to 10 days): Nausea, vomiting, diarrhea, rash erythema, edema, swelling, fatigue, muscle spasms, thrombocytopenia, pancytopenia, abdominal pain, headache, decreased appetite.

1,800 to 3,200 mg (as high as 3,200 mg daily for 6 days): Weakness, myalgia, increased CPK, increased bilirubin, GI pain.

6,400 mg (single dose): One case in the literature reported one patient who experienced nausea, vomiting, abdominal pain, pyrexia, facial swelling, neutrophil count decreased, increase transaminases.

8 to 10 g (single dose): Vomiting and GI pain have been reported.

A patient with myeloid blast crisis experienced Grade 1 elevations of serum creatinine, Grade 2 ascites and elevated liver transaminase levels, and Grade 3 elevations of bilirubin after inadvertently taking 1,200 mg of Gleevec daily for 6 days. Therapy was temporarily interrupted and complete reversal of all abnormalities occurred within 1 week. Treatment was resumed at a dose of 400 mg daily without recurrence of adverse reactions. Another patient developed severe muscle cramps after taking 1,600 mg of Gleevec daily for 6 days. Complete resolution of muscle cramps occurred following interruption of therapy and treatment was subsequently resumed. Another patient that was prescribed 400 mg daily, took 800 mg of Gleevec on Day 1 and 1,200 mg on Day 2. Therapy was interrupted, no adverse reactions occurred and the patient resumed therapy.

Pediatric Overdose

One 3 year old male exposed to a single dose of 400 mg experienced vomiting, diarrhea, and anorexia; and another 3 year old male exposed to a single dose of 980 mg experienced decreased white blood cell (WBC) count and diarrhea.

11 DESCRIPTION

Imatinib is a small molecule kinase inhibitor. Gleevec film-coated tablets are supplied as 100 mg and 400 mg tablets for oral administration. Each 100 mg tablet contains 119.5 mg of imatinib mesylate equivalent to 100 mg of imatinib free base. Each 400 mg tablet contains 478 mg of imatinib mesylate equivalent to 400 mg of imatinib free base. Imatinib mesylate is designated chemically as 4-[(4-Methyl-1-piperazinyl)methyl]-N-[4-methyl-3-[[4-(3-pyridinyl)-2-pyrimidinyl]amino]-phenyl]benzamide methanesulfonate and its structural formula is:

Imatinib mesylate is a white to off-white to brownish or yellowish tinged crystalline powder. Its molecular formula is C29H31N7O • CH4SO3 and its molecular weight is 589.7 g/mol. Imatinib mesylate is soluble in aqueous buffers less than or equal to pH 5.5 but is very slightly soluble to insoluble in neutral/alkaline aqueous buffers. In non-aqueous solvents, the drug substance is freely soluble to very slightly soluble in dimethyl sulfoxide, methanol, and ethanol, but is insoluble in n-octanol, acetone, and acetonitrile.

Inactive Ingredients: colloidal silicon dioxide (NF); crospovidone (NF); hydroxypropyl methylcellulose (USP); magnesium stearate (NF); and microcrystalline cellulose (NF). Tablet coating: ferric oxide, red (NF); ferric oxide, yellow (NF); hydroxypropyl methylcellulose (USP); polyethylene glycol (NF), and talc (USP).

12 CLINICAL PHARMACOLOGY

12.1 Mechanism of Action

Imatinib mesylate is a protein-tyrosine kinase inhibitor that inhibits the BCR-ABL tyrosine kinase, the constitutive abnormal tyrosine kinase created by the Philadelphia chromosome abnormality in CML. Imatinib inhibits proliferation and induces apoptosis in BCR-ABL positive cell lines as well as fresh leukemic cells from Philadelphia chromosome positive chronic myeloid leukemia. Imatinib inhibits colony formation in assays using ex vivo peripheral blood and bone marrow samples from CML patients.

In vivo, imatinib inhibits tumor growth of BCR-ABL transfected murine myeloid cells as well as BCR-ABL positive leukemia lines derived from CML patients in blast crisis.

Imatinib is also an inhibitor of the receptor tyrosine kinases for platelet-derived growth factor (PDGF) and stem cell factor (SCF), c-Kit, and inhibits PDGF- and SCF-mediated cellular events. In vitro, imatinib inhibits proliferation and induces apoptosis in GIST cells, which express an activating c-Kit mutation.

12.3 Pharmacokinetics

The pharmacokinetics of Gleevec have been evaluated in studies in healthy subjects and in population pharmacokinetic studies in over 900 patients. The pharmacokinetics of Gleevec are similar in CML and GIST patients.

Absorption and Distribution

Imatinib is well absorbed after oral administration with Cmax achieved within 2-4 hours post-dose. Mean absolute bioavailability is 98%. Mean imatinib AUC increases proportionally with increasing doses ranging from 25 mg to 1,000 mg. There is no significant change in the pharmacokinetics of imatinib on repeated dosing, and accumulation is 1.5- to 2.5-fold at steady state when Gleevec is dosed once daily. At clinically relevant concentrations of imatinib, binding to plasma proteins in in vitro experiments is approximately 95%, mostly to albumin and α1-acid glycoprotein.

Elimination

Metabolism

CYP3A4 is the major enzyme responsible for metabolism of imatinib. Other cytochrome P450 enzymes, such as CYP1A2, CYP2D6, CYP2C9, and CYP2C19, play a minor role in its metabolism. The main circulating active metabolite in humans is the N-demethylated piperazine derivative, formed predominantly by CYP3A4. It shows in vitro potency similar to the parent imatinib. The plasma AUC for this metabolite is about 15% of the AUC for imatinib. The plasma protein binding of N-demethylated metabolite CGP74588 is similar to that of the parent compound.

Excretion

Imatinib elimination is predominately in the feces, mostly as metabolites. Based on the recovery of compound(s) after an oral ^14C-labeled dose of imatinib, approximately 81% of the dose was eliminated within 7 days, in feces (68% of dose) and urine (13% of dose). Unchanged imatinib accounted for 25% of the dose (5% urine, 20% feces), the remainder being metabolites.

Following oral administration in healthy volunteers, the elimination half-lives of imatinib and its major active metabolite, the N-demethyl derivative (CGP74588), are approximately 18 and 40 hours, respectively.

Typically, clearance of imatinib in a 50-year-old patient weighing 50 kg is expected to be 8 L/h, while for a 50-year-old patient weighing 100 kg the clearance will increase to 14 L/h. The inter-patient variability of 40% in clearance does not warrant initial dose adjustment based on body weight and/or age but indicates the need for close monitoring for treatment-related toxicity.

Specific Populations

Hepatic Impairment

The effect of hepatic impairment on the pharmacokinetics of both imatinib and its major metabolite, CGP74588, was assessed in 84 patients with cancer and varying degrees of hepatic impairment [see Use in Specific Populations (8.6)] at imatinib doses ranging from 100 mg to 800 mg. Exposure to both imatinib and CGP74588 was comparable between each of the mildly and moderately hepatically-impaired groups and the normal group. Patients with severe hepatic impairment tend to have higher exposure to both imatinib and its metabolite than patients with normal hepatic function. At steady state, the mean Cmax/dose and AUC/dose for imatinib increased by about 63% and 45%, respectively, in patients with severe hepatic impairment compared to patients with normal hepatic function. The mean Cmax/dose and AUC/dose for CGP74588 increased by about 56% and 55%, respectively, in patients with severe hepatic impairment compared to patients with normal hepatic function. Dose reductions are necessary for patients with severe hepatic impairment [see Dosage and Administration (2.12)].

Renal Impairment

The effect of renal impairment on the pharmacokinetics of imatinib was assessed in 59 cancer patients with varying degrees of renal impairment [see Use in Specific Populations (8.7)] at single and steady state imatinib doses ranging from 100 to 800 mg/day. The mean exposure to imatinib (dose normalized AUC) in patients with mild and moderate renal impairment increased 1.5- to 2-fold compared to patients with normal renal function. The AUCs did not increase for doses greater than 600 mg in patients with mild renal impairment. The AUCs did not increase for doses greater than 400 mg in patients with moderate renal impairment. Two patients with severe renal impairment were dosed with 100 mg/day and their exposures were similar to those seen in patients with normal renal function receiving 400 mg/day. Dose reductions are necessary for patients with moderate and severe renal impairment [see Dosage and Administration (2.12)].

Pediatric Use

As in adult patients, imatinib was rapidly absorbed after oral administration in pediatric patients, with a Cmax of 2–4 hours. Apparent oral clearance was similar to adult values (11.0 L/hr/m^2 in children vs 10.0 L/hr/m^2 in adults), as was the half-life (14.8 hours in children vs 17.1 hours in adults). Dosing in children at both 260 mg/m^2 and 340 mg/m^2 achieved an AUC similar to the 400 mg dose in adults. The comparison of AUC on Day 8 vs Day 1 at 260 mg/m^2 and 340 mg/m^2 dose levels revealed a 1.5- and 2.2-fold drug accumulation, respectively, after repeated once-daily dosing. Mean imatinib AUC did not increase proportionally with increasing dose.

Based on pooled population pharmacokinetic analysis in pediatric patients with hematological disorders (CML, Ph+ ALL, or other hematological disorders treated with imatinib), clearance of imatinib increases with increasing BSA. After correcting for the BSA effect, other demographics, such as age, body weight, and body mass index did not have clinically significant effects on the exposure of imatinib. The analysis confirmed that exposure of imatinib in pediatric patients receiving 260 mg/m^2 once daily (not exceeding 400 mg once daily) or 340 mg/m^2 once daily (not exceeding 600 mg once daily) were similar to those in adult patients who received imatinib 400 mg or 600 mg once daily.

Drug Interaction Studies

Clinical Studies

Agents Inducing CYP3A Metabolism

Pretreatment of healthy volunteers with multiple doses of rifampin followed by a single dose of Gleevec, increased Gleevec oral-dose clearance by 3.8-fold, which significantly (p less than 0.05) decreased mean Cmax and AUC.

Similar findings were observed in patients receiving 400 to 1200 mg/day Gleevec concomitantly with enzyme-inducing anti-epileptic drugs (EIAED) (e.g., carbamazepine, oxcarbamazepine, phenytoin, fosphenytoin, phenobarbital, and primidone). The mean dose normalized AUC for imatinib in the patients receiving EIAED’s decreased by 73% compared to patients not receiving EIAED.

Concomitant administration of Gleevec and St. John’s Wort led to a 30% reduction in the AUC of imatinib.

Consider alternative therapeutic agents with less enzyme induction potential in patients when rifampin or other CYP3A4 inducers are indicated. Gleevec doses up to 1,200 mg/day (600 mg twice daily) have been given to patients receiving concomitant strong CYP3A4 inducers [see Dosage and Administration (2.12)].

Agents Inhibiting CYP3A Metabolism

There was a significant increase in exposure to imatinib (mean Cmax and AUC increased by 26% and 40%, respectively) in healthy subjects when Gleevec was coadministered with a single dose of ketoconazole (a CYP3A4 inhibitor). Caution is recommended when administering Gleevec with strong CYP3A4 inhibitors (e.g., ketoconazole, itraconazole, clarithromycin, atazanavir, indinavir, nefazodone, nelfinavir, ritonavir, saquinavir, telithromycin, and voriconazole). Grapefruit juice may also increase plasma concentrations of imatinib and should be avoided.

Interactions with Drugs Metabolized by CYP3A4

Gleevec increases the mean Cmax and AUC of simvastatin (CYP3A4 substrate) 2- and 3.5-fold, respectively, suggesting an inhibition of the CYP3A4 by Gleevec. Particular caution is recommended when administering Gleevec with CYP3A4 substrates that have a narrow therapeutic window (e.g., alfentanil, cyclosporine, diergotamine, ergotamine, fentanyl, pimozide, quinidine, sirolimus, or tacrolimus).

Gleevec will increase plasma concentration of other CYP3A4 metabolized drugs (e.g., triazolo-benzodiazepines, dihydropyridine calcium channel blockers, certain HMG-CoA reductase inhibitors, etc.).

Because warfarin is metabolized by CYP2C9 and CYP3A4, patients who require anticoagulation should receive low-molecular weight or standard heparin instead of warfarin.

Interactions with Drugs Metabolized by CYP2D6

Gleevec increased the mean Cmax and AUC of metoprolol by approximately 23% suggesting that Gleevec has a weak inhibitory effect on CYP2D6-mediated metabolism. No dose adjustment is necessary, however, caution is recommended when administering Gleevec with CYP2D6 substrates that have a narrow therapeutic window.

Interactions with Acetaminophen

Coadministration of Gleevec (400 mg/day for 8 days) with acetaminophen (1,000 mg single dose on Day 8) in patients with CML did not result in any changes in the pharmacokinetics of acetaminophen. Gleevec pharmacokinetics were not altered in the presence of single-dose acetaminophen. There is no pharmacokinetic or safety data on the concomitant use of Gleevec at doses greater than 400 mg/day or the chronic use of concomitant acetaminophen and Gleevec.

In Vitro Studies

Cytochrome P450 (CYP450) Enzymes: Imatinib inhibits CYP2C9 and CYP2D6.

Transporter Systems: Imatinib is a substrate of BCRP, P-gp, OATP1A2, OATP1B3, and OCT1. Imatinib inhibits BCRP, BSEP, P-gp, MATE1, MATE2-K, OCT1, and OCT2.

13 NONCLINICAL TOXICOLOGY

13.1 Carcinogenesis, Mutagenesis, Impairment of Fertility

In the 2-year rat carcinogenicity study administration of imatinib at 15, 30, and 60 mg/kg/day resulted in a statistically significant reduction in the longevity of males at 60 mg/kg/day and females at greater than or equal to 30 mg/kg/day. Target organs for neoplastic changes were the kidneys (renal tubule and renal pelvis), urinary bladder, urethra, preputial and clitoral gland, small intestine, parathyroid glands, adrenal glands and non-glandular stomach. Neoplastic lesions were not seen at: 30 mg/kg/day for the kidneys, urinary bladder, urethra, small intestine, parathyroid glands, adrenal glands and non-glandular stomach, and 15 mg/kg/day for the preputial and clitoral gland. The papilloma/carcinoma of the preputial/clitoral gland were noted at 30 and 60 mg/kg/day, representing approximately 0.5 to 4 or 0.3 to 2.4 times the human daily exposure (based on AUC) at 400 mg/day or 800 mg/day, respectively, and 0.4 to 3.0 times the daily exposure in children (based on AUC) at 340 mg/m^2. The renal tubule adenoma/carcinoma, renal pelvis transitional cell neoplasms, the urinary bladder and urethra transitional cell papillomas, the small intestine adenocarcinomas, the parathyroid glands adenomas, the benign and malignant medullary tumors of the adrenal glands and the non-glandular stomach papillomas/carcinomas were noted at 60 mg/kg/day. The relevance of these findings in the rat carcinogenicity study for humans is not known. Positive genotoxic effects were obtained for imatinib in an in vitro mammalian cell assay (Chinese hamster ovary) for clastogenicity (chromosome aberrations) in the presence of metabolic activation. Two intermediates of the manufacturing process, which are also present in the final product, are positive for mutagenesis in the Ames assay. One of these intermediates was also positive in the mouse lymphoma assay. Imatinib was not genotoxic when tested in an in vitro bacterial cell assay (Ames test), an in vitro mammalian cell assay (mouse lymphoma) and an in vivo rat micronucleus assay.

In a study of fertility, male rats were dosed for 70 days prior to mating and female rats were dosed 14 days prior to mating and through to gestational Day 6. Testicular and epididymal weights and percent motile sperm were decreased at 60 mg/kg, approximately three-fourths the maximum clinical dose of 800 mg/day based on BSA. This was not seen at doses less than or equal to 20 mg/kg (one-fourth the maximum human dose of 800 mg). The fertility of male and female rats was not affected.

Fertility was not affected in the preclinical fertility and early embryonic development study although lower testes and epididymal weights as well as a reduced number of motile sperm were observed in the high dose males rats. In the preclinical pre- and postnatal study in rats, fertility in the first generation offspring was also not affected by imatinib mesylate.

13.2 Animal Toxicology and/or Pharmacology

Toxicities from Long-Term Use

It is important to consider potential toxicities suggested by animal studies, specifically, liver, kidney, and cardiac toxicity and immunosuppression. Severe liver toxicity was observed in dogs treated for 2 weeks, with elevated liver enzymes, hepatocellular necrosis, bile duct necrosis, and bile duct hyperplasia. Renal toxicity was observed in monkeys treated for 2 weeks, with focal mineralization and dilation of the renal tubules and tubular nephrosis. Increased blood urea nitrogen (BUN) and creatinine were observed in several of these animals. An increased rate of opportunistic infections was observed with chronic imatinib treatment in laboratory animal studies. In a 39 week monkey study, treatment with imatinib resulted in worsening of normally suppressed malarial infections in these animals. Lymphopenia was observed in animals (as in humans). Additional long-term toxicities were identified in a 2-year rat study. Histopathological examination of the treated rats that died on study revealed cardiomyopathy (both sexes), chronic progressive nephropathy (females) and preputial gland papilloma as principal causes of death or reasons for sacrifice. Non-neoplastic lesions seen in this 2-year study which were not identified in earlier preclinical studies were the cardiovascular system, pancreas, endocrine organs, and teeth. The most important changes included cardiac hypertrophy and dilatation, leading to signs of cardiac insufficiency in some animals.

14 CLINICAL STUDIES

14.1 Chronic Myeloid Leukemia

Chronic Phase, Newly Diagnosed:

An open-label, multicenter, international randomized Phase 3 study (Gleevec versus IFN+Ara-C) has been conducted in patients with newly diagnosed Philadelphia chromosome positive (Ph+) chronic myeloid leukemia (CML) in chronic phase. This study compared treatment with either single-agent Gleevec or a combination of interferon-alpha (IFN) plus cytarabine (Ara-C). Patients were allowed to cross over to the alternative treatment arm if they failed to show a complete hematologic response (CHR) at 6 months, a major cytogenetic response (MCyR) at 12 months, or if they lost a CHR or MCyR. Patients with increasing WBC or severe intolerance to treatment were also allowed to cross over to the alternative treatment arm with the permission of the study monitoring committee (SMC). In the Gleevec arm, patients were treated initially with 400 mg daily. Dose escalations were allowed from 400 mg daily to 600 mg daily, then from 600 mg daily to 800 mg daily. In the IFN arm, patients were treated with a target dose of IFN of 5 MIU/m^2/day subcutaneously in combination with subcutaneous Ara-C 20 mg/m^2/day for 10 days/month.

A total of 1106 patients were randomized from 177 centers in 16 countries, 553 to each arm. Baseline characteristics were well balanced between the two arms. Median age was 51 years (range, 18 to 70 years), with 21.9% of patients greater than or equal to 60 years of age. There were 59% males and 41% females; 89.9% Caucasian and 4.7% black patients. At the cut-off for this analysis (7 years after last patient had been recruited), the median duration of first-line treatment was 82 and 8 months in the Gleevec and IFN arm, respectively. The median duration of second-line treatment with Gleevec was 64 months. Sixty percent of patients randomized to Gleevec are still receiving first-line treatment. In these patients, the average dose of Gleevec was 403 mg ± 57 mg. Overall, in patients receiving first line Gleevec, the average daily dose delivered was 406 mg ± 76 mg. Due to discontinuations and cross-overs, only 2% of patients randomized to IFN were still on first-line treatment. In the IFN arm, withdrawal of consent (14%) was the most frequent reason for discontinuation of first-line therapy, and the most frequent reason for cross over to the Gleevec arm was severe intolerance to treatment (26%) and progression (14%).

- The primary efficacy endpoint of the study was progression-free survival (PFS). Progression was defined as any of the following events: progression to accelerated phase or blast crisis (AP/BC), death, loss of CHR or MCyR, or in patients not achieving a CHR an increasing WBC despite appropriate therapeutic management. The protocol specified that the progression analysis would compare the intent to treat (ITT) population: patients randomized to receive Gleevec were compared with patients randomized to receive IFN. Patients that crossed over prior to progression were not censored at the time of cross-over, and events that occurred in these patients following cross-over were attributed to the original randomized treatment. The estimated rate of progression-free survival at 84 months in the ITT population was 81.2% [95% CI: 78, 85] in the Gleevec arm and 60.6% [56, 65] in the IFN arm (p less than 0.0001, log-rank test), (Figure 1). With 7 years follow up there were 93 (16.8%) progression events in the Gleevec arm: 37 (6.7%) progression to AP/BC, 31 (5.6%) loss of MCyR, 15 (2.7%) loss of CHR or increase in WBC and 10 (1.8%) CML unrelated deaths. In contrast, there were 165 (29.8%) events in the IFN+Ara-C arm of which 130 occurred during first-line treatment with IFN-Ara-C. The estimated rate of patients free of progression to accelerated phase (AP) or blast crisis (BC) at 84 months was 92.5% [90, 95] in the Gleevec arm compared to the 85.1%, [82, 89] (p less than or equal to 0.001) in the IFN arm, (Figure 2). The annual rates of any progression events have decreased with time on therapy. The probability of remaining progression free at 60 months was 95% for patients who were in complete cytogenetic response (CCyR) with molecular response (greater than or equal to 3 log reduction in BCR-ABL transcripts as measured by quantitative reverse transcriptase polymerase chain reaction) at 12 months, compared to 89% for patients in CCyR but without a major molecular response and 70% in patients who were not in CCyR at this time point (p less than 0.001).

Figure 1: Progression Free Survival (ITT Principle)

Figure 2: Time to Progression to AP or BC (ITT Principle)

A total of 71 (12.8%) and 85 (15.4%) patients died in the Gleevec and IFN+Ara-C group, respectively. At 84 months the estimated overall survival is 86.4% (83, 90) vs 83.3% (80, 87) in the randomized Gleevec and the IFN+Ara-C group, respectively (p = 0.073 log-rank test). The hazard ratio is 0.750 with 95% CI 0.547-1.028. This time-to-event endpoint may be affected by the high crossover rate from IFN+Ara-C to Gleevec. Major cytogenetic response, hematologic response, evaluation of minimal residual disease (molecular response), time to accelerated phase or blast crisis and survival were main secondary endpoints. Response data are shown in Table 18. Complete hematologic response, major cytogenetic response and CCyR were also statistically significantly higher in the Gleevec arm compared to the IFN + Ara-C arm (no cross-over data considered for evaluation of responses). Median time to CCyR in the 454 responders was 6 months (range, 2 to 64 months, 25th to 75th percentiles = 3 to 11 months) with 10% of responses seen only after 22 months of therapy.

Table 18: Response in Newly Diagnosed CML Study (84-Month Data)
Best response rate | Gleevec n = 553 | IFN+Ara−C n = 553
Hematologic response^1
CHR rate n (%) | 534 (96.6%)* | 313 (56.6%)*
[95% CI] | [94.7%, 97.9%] | [52.4%, 60.8%]
Cytogenetic response^2
Major cytogenetic response n (%) | 472 (85.4%)* | 93 (16.8%)*
[95% CI] | [82.1%, 88.2%] | [13.8%, 20.2%]
Unconfirmed^3 | 88.6%* | 23.3%*
Complete cytogenetic response n (%) | 413 (74.7%)* | 36 (6.5%)*
[95% CI] | [70.8, 78.3] | [4.6, 8.9]
Unconfirmed^3 | 82.5%* | 11.6%*
*p less than 0.001, Fischer’s exact test.
^1 Hematologic response criteria (all responses to be confirmed after greater than or equal to 4 weeks):
WBC less than 10 x 10^9/L, platelet less than 450 x 10^9/L, myelocyte + metamyelocyte less than 5% in blood, no blasts and promyelocytes in blood, no extramedullary involvement.
^2 Cytogenetic response criteria (confirmed after greater than or equal to 4 weeks): complete (0% Ph+ metaphases) or partial (1%-35%). A major response (0%-35%) combines both complete and partial responses.
^3 Unconfirmed cytogenetic response is based on a single bone marrow cytogenetic evaluation, therefore unconfirmed complete or partial cytogenetic responses might have had a lesser cytogenetic response on a subsequent bone marrow evaluation.

Molecular response was defined as follows: in the peripheral blood, after 12 months of therapy, reduction of greater than or equal to 3 logarithms in the amount of BCR-ABL transcripts (measured by real-time quantitative reverse transcriptase PCR assay) over a standardized baseline. Molecular response was only evaluated in a subset of patients who had a CCyR by 12 months or later (N = 333). The molecular response rate in patients who had a CCyR in the Gleevec arm was 59% at 12 months and 72% at 24 months.

Physical, functional, and treatment-specific biologic response modifier scales from the FACT-BRM (Functional Assessment of Cancer Therapy - Biologic Response Modifier) instrument were used to assess patient-reported general effects of interferon toxicity in 1,067 patients with CML in chronic phase. After one month of therapy to 6 months of therapy, there was a 13% to 21% decrease in median index from baseline in patients treated with IFN, consistent with increased symptoms of IFN toxicity. There was no apparent change from baseline in median index for patients treated with Gleevec.

An open-label, multicenter, randomized trial (Gleevec versus nilotinib) was conducted to determine the efficacy of Gleevec versus nilotinib in adult patients with cytogenetically confirmed, newly diagnosed Ph+ CML-CP. Patients were within 6 months of diagnosis and were previously untreated for CML-CP, except for hydroxyurea and/or anagrelide. Efficacy was based on a total of 846 patients: 283 patients in the Gleevec 400 mg once daily group, 282 patients in the nilotinib 300 mg twice daily group, 281 patients in the nilotinib 400 mg twice daily group.

Median age was 46 years in the Gleevec group and 47 years in both nilotinib groups, with 12%, 13%, and 10% of patients greater than or equal to 65 years of age in Gleevec 400 mg once daily, nilotinib 300 mg twice daily and nilotinib 400 mg twice daily treatment groups, respectively. There were slightly more male than female patients in all groups (56%, 56%, and 62% in Gleevec 400 mg once daily, nilotinib 300 mg twice daily and nilotinib 400 mg twice-daily treatment groups, respectively). More than 60% of all patients were Caucasian, and 25% were Asian.

The primary data analysis was performed when all 846 patients completed 12 months of treatment or discontinued earlier. Subsequent analyses were done when patients completed 24, 36, 48, and 60 months of treatment or discontinued earlier. The median time on treatment was approximately 61 months in all three treatment groups.

The primary efficacy endpoint was major molecular response (MMR) at 12 months after the start of study medication. MMR was defined as less than or equal to 0.1% BCR-ABL/ABL % by international scale measured by RQ-PCR, which corresponds to a greater than or equal to 3 log reduction of BCR-ABL transcript from standardized baseline. Efficacy endpoints are summarized in Table 19.

Twelve patients in the Gleevec arm progressed to either accelerated phase or blast crises (7 patients within first 6 months, 2 patients within 6 to 12 months, 2 patients within 12 to 18 months and 1 patient within 18 to 24 months) while two patients on the nilotinib arm progressed to either accelerated phase or blast crisis (both within the first 6 months of treatment).

Table 19: Efficacy (MMR and CCyR) of Gleevec Compared to Nilotinib in Newly Diagnosed Ph+ CML-CP
 | Gleevec 400 mg once daily | Nilotinib 300 mg twice daily
 | N = 283 | N = 282
MMR at 12 months (95% CI) | 22% (17.6, 27.6) | 44% (38.4, 50.3)
P-Valuea | < 0.0001
CCyRb by 12 months (95% CI) | 65% (59.2, 70.6) | 80% (75.0, 84.6)
MMR at 24 months (95% CI) | 38% (31.8, 43.4) | 62% (55.8, 67.4)
CCyRb by 24 months (95% CI) | 77% (71.7, 81.8) | 87% (82.4, 90.6)
Abbreviations: CCyR, complete cytogenetic response; MMR, major molecular response; Ph+ CML-CP, Philadelphia chromosome positive chronic myeloid leukemia-chronic phase.
aCMH test stratified by Sokal risk group.
bCCyR: 0% Ph+ metaphases. Cytogenetic responses were based on the percentage of Ph-positive metaphases among greater than or equal to 20 metaphase cells in each bone marrow sample.

By 60 months, MMR was achieved by 60% of patients on Gleevec and 77% of patients on nilotinib.

Median overall survival was not reached in either arm. At the time of the 60-month final analysis, the estimated survival rate was 91.7% for patients on Gleevec and 93.7% for patients on nilotinib.

Late Chronic Phase CML and Advanced Stage CML: Three international, open-label, single-arm Phase 2 studies were conducted to determine the safety and efficacy of Gleevec in patients with Ph+ CML: 1) in the chronic phase after failure of IFN therapy, 2) in accelerated phase disease, or 3) in myeloid blast crisis. About 45% of patients were women and 6% were black. In clinical studies, 38% to 40% of patients were greater than or equal to 60 years of age and 10% to 12% of patients were greater than or equal to 70 years of age.

Chronic Phase, Prior Interferon-Alpha Treatment: 532 patients were treated at a starting dose of 400 mg; dose escalation to 600 mg was allowed. The patients were distributed in three main categories according to their response to prior interferon: failure to achieve (within 6 months), or loss of a complete hematologic response (29%), failure to achieve (within 1 year) or loss of a major cytogenetic response (35%), or intolerance to interferon (36%). Patients had received a median of 14 months of prior IFN therapy at doses greater than or equal to 25 x 10^6 units/week and were all in late chronic phase, with a median time from diagnosis of 32 months. Effectiveness was evaluated on the basis of the rate of hematologic response and by bone marrow exams to assess the rate of major cytogenetic response (up to 35% Ph+ metaphases) or CCyR (0% Ph+ metaphases). Median duration of treatment was 29 months with 81% of patients treated for greater than or equal to 24 months (maximum = 31.5 months). Efficacy results are reported in Table 20. Confirmed major cytogenetic response rates were higher in patients with IFN intolerance (66%) and cytogenetic failure (64%), than in patients with hematologic failure (47%). Hematologic response was achieved in 98% of patients with cytogenetic failure, 94% of patients with hematologic failure, and 92% of IFN-intolerant patients.

Accelerated Phase: 235 patients with accelerated phase disease were enrolled. These patients met one or more of the following criteria: greater than or equal to 15% - less than 30% blasts in PB or BM; greater than or equal to 30% blasts + promyelocytes in PB or BM; greater than or equal to 20% basophils in PB; and less than 100 x 10^9/L platelets. The first 77 patients were started at 400 mg, with the remaining 158 patients starting at 600 mg.

Effectiveness was evaluated primarily on the basis of the rate of hematologic response, reported as either complete hematologic response, no evidence of leukemia (i.e., clearance of blasts from the marrow and the blood, but without a full peripheral blood recovery as for complete responses), or return to chronic phase CML. Cytogenetic responses were also evaluated. Median duration of treatment was 18 months with 45% of patients treated for greater than or equal to 24 months (maximum = 35 months). Efficacy results are reported in Table 20. Response rates in accelerated phase CML were higher for the 600 mg dose group than for the 400 mg group: hematologic response (75% vs 64%), confirmed and unconfirmed major cytogenetic response (31% vs 19%).

Myeloid Blast Crisis: 260 patients with myeloid blast crisis were enrolled. These patients had greater than or equal to 30% blasts in PB or BM and/or extramedullary involvement other than spleen or liver; 95 (37%) had received prior chemotherapy for treatment of either accelerated phase or blast crisis (“pretreated patients”) whereas 165 (63%) had not (“untreated patients”). The first 37 patients were started at 400 mg; the remaining 223 patients were started at 600 mg.

Effectiveness was evaluated primarily on the basis of rate of hematologic response, reported as either complete hematologic response, no evidence of leukemia, or return to chronic phase CML using the same criteria as for the study in accelerated phase. Cytogenetic responses were also assessed. Median duration of treatment was 4 months with 21% of patients treated for greater than or equal to 12 months and 10% for greater than or equal to 24 months (maximum = 35 months). Efficacy results are reported in Table 20. The hematologic response rate was higher in untreated patients than in treated patients (36% vs 22%, respectively) and in the group receiving an initial dose of 600 mg rather than 400 mg (33% vs 16%). The confirmed and unconfirmed major cytogenetic response rate was also higher for the 600-mg dose group than for the 400-mg dose group (17% vs 8%).

Table 20: Response in Chronic Myeloid Leukemia Studies
 | Chronic phase IFN failure (n = 532) | Accelerated phase (n = 235) | Myeloid blast crisis (n = 260)
 |  | 600 mg n = 158 | 600 mg n = 223
 | 400 mg | 400 mg n = 77 | 400 mg n = 37
 | % of patients [CI 95%]
Hematologic response^1 | 95% [92.3−96.3] | 71% [64.8−76.8] | 31% [25.2−36.8]
Complete hematologic response (CHR) | 95% | 38% | 7%
No evidence of leukemia (NEL) | Not applicable | 13% | 5%
Return to chronic phase (RTC) | Not applicable | 20% | 18%
Major cytogenetic response^2 | 60% [55.3−63.8] | 21% [16.2−27.1] | 7% [4.5−11.2]
(Unconfirmed^3) | (65%) | (27%) | (15%)
Complete^4 (Unconfirmed^3) | 39% (47%) | 16% (20%) | 2% (7%)
Abbreviations: BM, bone marrow; PB, peripheral blood.
^1 Hematologic response criteria (all responses to be confirmed after greater than or equal to 4 weeks):
CHR: Chronic phase study [WBC less than 10 x 10^9/L, platelet less than 450 x 10^9/L, myelocytes + metamyelocytes less than 5% in blood, no blasts and promyelocytes in blood, basophils less than 20%, no extramedullary involvement] and in the accelerated and blast crisis studies [absolute neutrophil count (ANC) greater than or equal to 1.5 x 10^9/L, platelets greater than or equal to 100 x 10^9/L, no blood blasts, BM blasts less than 5% and no extramedullary disease].
NEL: Same criteria as for CHR but ANC greater than or equal to 1 x 10^9/L and platelets greater than or equal to 20 x 10^9/L (accelerated and blast crisis studies).
RTC: less than 15% blasts BM and PB, less than 30% blasts + promyelocytes in BM and PB, less than 20% basophils in PB, no extramedullary disease other than spleen and liver (accelerated and blast crisis studies).
^2 Cytogenetic response criteria (confirmed after greater than or equal to 4 weeks): complete (0% Ph+ metaphases) or partial (1%-35%). A major response (0%-35%) combines both complete and partial responses.
^3 Unconfirmed cytogenetic response is based on a single bone marrow cytogenetic evaluation, therefore unconfirmed complete or partial cytogenetic responses might have had a lesser cytogenetic response on a subsequent bone marrow evaluation.
^4 Complete cytogenetic response confirmed by a second bone marrow cytogenetic evaluation performed at least 1 month after the initial bone marrow study.

The median time to hematologic response was 1 month. In late chronic phase CML, with a median time from diagnosis of 32 months, an estimated 87.8% of patients who achieved MCyR maintained their response 2 years after achieving their initial response. After 2 years of treatment, an estimated 85.4% of patients were free of progression to AP or BC, and estimated overall survival was 90.8% [88.3, 93.2]. In accelerated phase, median duration of hematologic response was 28.8 months for patients with an initial dose of 600 mg (16.5 months for 400 mg). An estimated 63.8% of patients who achieved MCyR were still in response 2 years after achieving initial response. The median survival was 20.9 [13.1, 34.4] months for the 400 mg group and was not yet reached for the 600 mg group (p = 0.0097). An estimated 46.2% [34.7, 57.7] vs 65.8% [58.4, 73.3] of patients were still alive after 2 years of treatment in the 400 mg vs 600 mg dose groups, respectively. In blast crisis, the estimated median duration of hematologic response is 10 months. An estimated 27.2% [16.8, 37.7] of hematologic responders maintained their response 2 years after achieving their initial response. Median survival was 6.9 [5.8, 8.6] months, and an estimated 18.3% [13.4, 23.3] of all patients with blast crisis were alive 2 years after start of study.

Efficacy results were similar in men and women and in patients younger and older than age 65. Responses were seen in black patients, but there were too few black patients to allow a quantitative comparison.

14.2 Pediatric CML

A total of 51 pediatric patients with newly diagnosed and untreated CML in chronic phase were enrolled in an open-label, multicenter, single-arm Phase 2 trial. Patients were treated with Gleevec 340 mg/m^2/day, with no interruptions in the absence of dose limiting toxicity. Complete hematologic response (CHR) was observed in 78% of patients after 8 weeks of therapy. The complete cytogenetic response rate (CCyR) was 65%, comparable to the results observed in adults. Additionally, partial cytogenetic response (PCyR) was observed in 16%. The majority of patients who achieved a CCyR developed the CCyR between Months 3 and 10 with a median time to response based on the Kaplan-Meier estimate of 6.74 months. Patients were allowed to be removed from protocol therapy to undergo alternative therapy, including hematopoietic stem cell transplantation. Thirty-one children received stem cell transplantation. Of the 31 children, 5 were transplanted after disease progression on study and 1 withdrew from study during first week treatment and received transplant approximately 4 months after withdrawal. Twenty-five children withdrew from protocol therapy to undergo stem cell transplant after receiving a median of 9 twenty-eight day courses (range, 4 to 24). Of the 25 patients 13 (52%) had CCyR and 5 (20%) had PCyR at the end of protocol therapy.

One open-label, single-arm study enrolled 14 pediatric patients with Ph+ chronic phase CML recurrent after stem cell transplant or resistant to interferon-alpha therapy. These patients had not previously received Gleevec and ranged in age from 3 to 20 years old; 3 were 3 to 11 years old, 9 were 12 to 18 years old, and 2 were greater than 18 years old. Patients were treated at doses of 260 mg/m^2/day (n = 3), 340 mg/m^2/day (n = 4), 440 mg/m^2/day (n = 5) and 570 mg/m^2/day (n = 2). In the 13 patients for whom cytogenetic data are available, 4 achieved a major cytogenetic response, 7 achieved a CCyR, and 2 had a minimal cytogenetic response.

In a second study, 2 of 3 patients with Ph+ chronic phase CML resistant to interferon-alpha therapy achieved a CCyR at doses of 242 and 257 mg/m^2/day.

14.3 Acute Lymphoblastic Leukemia

A total of 48 Philadelphia chromosome positive acute lymphoblastic leukemia (Ph+ ALL) patients with relapsed/refractory disease were studied, 43 of whom received the recommended Gleevec dose of 600 mg/day. In addition 2 patients with relapsed/refractory Ph+ ALL received Gleevec 600 mg/day in a Phase 1 study.

Confirmed and unconfirmed hematologic and cytogenetic response rates for the 43 relapsed/refractory Ph+ ALL Phase 2 study patients and for the 2 Phase 1 patients are shown in Table 21. The median duration of hematologic response was 3.4 months and the median duration of MCyR was 2.3 months.

Table 21: Effect of Gleevec on Relapsed/Refractory Ph+ ALL
 | Phase 2 study (N = 43) n (%) | Phase 1 study (N = 2) n (%)
CHR | 8 (19) | 2 (100)
NEL | 5 (12)
RTC/PHR | 11 (26)
MCyR | 15 (35)
CCyR | 9 (21)
PCyR | 6 (14)
Abbreviations: CCyR, complete cytogenetic response; CHR, complete hematologic response; MCyR, major cytogenetic response; NEL, no evidence of leukemia; PCyR, partial cytogenic response; Ph+ ALL, Philadelphia chromosome positive acute lymphoblastic leukemia; PHR, partial hematologic response; RTC, return to chronic phase.

14.4 Pediatric ALL

Pediatric and young adult patients with very high risk ALL, defined as those with an expected 5-year event-free survival (EFS) less than 45%, were enrolled after induction therapy on a multicenter, non-randomized cooperative group pilot protocol.

The safety and effectiveness of Gleevec (340 mg/m^2/day) in combination with intensive chemotherapy was evaluated in a subgroup of patients with Ph+ ALL. The protocol included intensive chemotherapy and hematopoietic stem cell transplant after 2 courses of chemotherapy for patients with an appropriate HLA-matched family donor. There were 92 eligible patients with Ph+ ALL enrolled. The median age was 9.5 years (1 to 21 years: 2.2% between 1 and less than 2 years, 56.5% between 2 and less than 12 years, 34.8% between 12 and less than 18 years, and 6.5% between 18 and 21 years). Sixty-four percent were male, 75% were white, 9% were Asian/Pacific Islander, and 5% were black. In 5 successive cohorts of patients, Gleevec exposure was systematically increased by earlier introduction and prolonged duration. Cohort 1 received the lowest intensity and cohort 5 received the highest intensity of Gleevec exposure.

There were 50 patients with Ph+ ALL assigned to cohort 5 all of whom received Gleevec plus chemotherapy; 30 were treated exclusively with chemotherapy and Gleevec and 20 received chemotherapy plus Gleevec and then underwent hematopoietic stem cell transplant, followed by further Gleevec treatment. Patients in cohort 5 treated with chemotherapy received continuous daily exposure to Gleevec beginning in the first course of post induction chemotherapy continuing through maintenance cycles 1 through 4 chemotherapy. During maintenance cycles 5 through 12, Gleevec was administered 28 days out of the 56 day cycle. Patients who underwent hematopoietic stem cell transplant received 42 days of Gleevec prior to HSCT, and 28 weeks (196 days) of Gleevec after the immediate post transplant period. The estimated 4-year EFS of patients in cohort 5 was 70% (95% CI: 54, 81). The median follow-up time for EFS at data cutoff in cohort 5 was 40.5 months.

14.5 Myelodysplastic/Myeloproliferative Diseases

An open-label, multicenter, Phase 2 clinical trial was conducted testing Gleevec in diverse populations of patients suffering from life-threatening diseases associated with Abl, Kit or PDGFR protein tyrosine kinases. This study included 7 patients with MDS/MPD. These patients were treated with Gleevec 400 mg daily. The ages of the enrolled patients ranged from 20 to 86 years. A further 24 patients with MDS/MPD aged 2 to 79 years were reported in 12 published case reports and a clinical study. These patients also received Gleevec at a dose of 400 mg daily with the exception of three patients who received lower doses. Of the total population of 31 patients treated for MDS/MPD, 14 (45%) achieved a complete hematological response and 12 (39%) a major cytogenetic response (including 10 with a CCyR). Sixteen patients had a translocation, involving chromosome 5q33 or 4q12, resulting in a PDGFR gene re-arrangement. All of these patients responded hematologically (13 completely). Cytogenetic response was evaluated in 12 out of 14 patients, all of whom responded (10 patients completely). Only 1 (7%) out of the 14 patients without a translocation associated with PDGFR gene re-arrangement achieved a complete hematological response and none achieved a major cytogenetic response. A further patient with a PDGFR gene re-arrangement in molecular relapse after bone marrow transplant responded molecularly. Median duration of therapy was 12.9 months (0.8 to 26.7) in the 7 patients treated within the Phase 2 study and ranged between 1 week and more than 18 months in responding patients in the published literature. Results are provided in Table 22. Response durations of Phase 2 study patients ranged from 141+ days to 457+ days.

Table 22: Response in MDS/MPD
 | Number of patients | Complete hematologic response | Major cytogenetic response
 | N | N (%) | N (%)
Overall population | 31 | 14 (45) | 12 (39)
Chromosome 5 translocation | 14 | 11 (79) | 11 (79)
Chromosome 4 translocation | 2 | 2 (100) | 1 (50)
Others/no translocation | 14 | 1 (7) | 0
Molecular relapse | 1 | NE | NE
Abbreviations: NE, not evaluable; MDS/MPD, myelodysplastic/myeloproliferative disease.

14.6 Aggressive Systemic Mastocytosis

One open-label, multicenter, Phase 2 study was conducted testing Gleevec in diverse populations of patients with life-threatening diseases associated with Abl, Kit or PDGFR protein tyrosine kinases. This study included 5 patients with ASM treated with 100 mg to 400 mg of Gleevec daily. These 5 patients ranged from 49 to 74 years of age. In addition to these 5 patients, 10 published case reports and case series describe the use of Gleevec in 23 additional patients with ASM aged 26 to 85 years who also received 100 mg to 400 mg of Gleevec daily.

Cytogenetic abnormalities were evaluated in 20 of the 28 ASM patients treated with Gleevec from the published reports and in the Phase 2 study. Seven of these 20 patients had the FIP1L1-PDGFRα fusion kinase (or CHIC2 deletion). Patients with this cytogenetic abnormality were predominantly males and had eosinophilia associated with their systemic mast cell disease. Two patients had a Kit mutation in the juxtamembrane region (one Phe522Cys and one K509I) and four patients had a D816V c-Kit mutation (not considered sensitive to Gleevec), one with concomitant CML.

Of the 28 patients treated for ASM, 8 (29%) achieved a complete hematologic response and 9 (32%) a partial hematologic response (PHR) (61% overall response rate). Median duration of Gleevec therapy for the 5 ASM patients in the Phase 2 study was 13 months (range, 1.4 to 22.3 months) and between 1 month and more than 30 months in the responding patients described in the published medical literature. A summary of the response rates to Gleevec in ASM is provided in Table 23. Response durations of literature patients ranged from 1+ to 30+ months.

Table 23: Response in ASM
Cytogenetic abnormality | Number of patients N | Complete hematologic response N (%) | Partial hematologic response N (%)
FIP1L1-PDGFRα fusion kinase (or CHIC2 deletion) | 7 | 7 (100) | 0
Juxtamembrane mutation | 2 | 0 | 2 (100)
Unknown or no cytogenetic abnormality detected | 15 | 0 | 7 (44)
D816V mutation | 4 | 1* (25) | 0
Total | 28 | 8 (29) | 9 (32)
Abbreviations: ASM, aggressive systemic mastocytosis; PDGFR, platelet-derived growth factor receptor.
*Patient had concomitant chronic myeloid leukemia CML and ASM.

Gleevec has not been shown to be effective in patients with less aggressive forms of systemic mastocytosis (SM). Gleevec is therefore not recommended for use in patients with cutaneous mastocytosis, indolent systemic mastocytosis (smoldering SM or isolated bone marrow mastocytosis), SM with an associated clonal hematological non-mast cell lineage disease, mast cell leukemia, mast cell sarcoma or extracutaneous mastocytoma. Patients that harbor the D816V mutation of c-Kit are not sensitive to Gleevec and should not receive Gleevec.

14.7 Hypereosinophilic Syndrome/Chronic Eosinophilic Leukemia

One open-label, multicenter, Phase 2 study was conducted testing Gleevec in diverse populations of patients with life-threatening diseases associated with Abl, Kit or PDGFR protein tyrosine kinases. This study included 14 patients with Hypereosinophilic Syndrome/Chronic Eosinophilic Leukemia (HES/CEL). HES patients were treated with 100 mg to 1,000 mg of Gleevec daily. The ages of these patients ranged from 16 to 64 years. A further 162 patients with HES/CEL aged 11 to 78 years were reported in 35 published case reports and case series. These patients received Gleevec at doses of 75 mg to 800 mg daily. Hematologic response rates are summarized in Table 24. Response durations for literature patients ranged from 6+ weeks to 44 months.

Table 24: Response in HES/CEL
Cytogenetic abnormality | Number of patients | Complete hematological response N (%) | Partial hematological response N (%)
Positive FIP1L1-PDGFRα fusion kinase | 61 | 61 (100) | 0
Negative FIP1L1-PDGFRα fusion kinase | 56 | 12 (21) | 9 (16)
Unknown cytogenetic abnormality | 59 | 34 (58) | 7 (12)
Total | 176 | 107 (61) | 23 (13)
Abbreviations: CEL, chronic eosinophilic leukemia; HES, hypereosinophilic syndrome; PDGFR, platelet-derived growth factor receptor.

14.8 Dermatofibrosarcoma Protuberans

Dermatofibrosarcoma Protuberans (DFSP) is a cutaneous soft tissue sarcoma. It is characterized by a translocation of chromosomes 17 and 22 that results in the fusion of the collagen type 1 alpha 1 gene and the PDGF B gene.

An open-label, multicenter, Phase 2 study was conducted testing Gleevec in a diverse population of patients with life-threatening diseases associated with Abl, Kit or PDGFR protein tyrosine kinases. This study included 12 patients with DFSP who were treated with Gleevec 800 mg daily (age range, 23 to 75 years). DFSP was metastatic, locally recurrent following initial surgical resection and not considered amenable to further surgery at the time of study entry. A further 6 DFSP patients treated with Gleevec are reported in 5 published case reports, their ages ranging from 18 months to 49 years. The total population treated for DFSP therefore comprises 18 patients, 8 of them with metastatic disease. The adult patients reported in the published literature were treated with either 400 mg (4 cases) or 800 mg (1 case) Gleevec daily. A single pediatric patient received 400 mg/m^2/daily, subsequently increased to 520 mg/m^2/daily. Ten patients had the PDGF B gene rearrangement, 5 had no available cytogenetics and 3 had complex cytogenetic abnormalities. Responses to treatment are described in Table 25.

Table 25: Response in DFSP
 | Number of patients (n = 18) | %
Complete response | 7 | 39
Partial response* | 8 | 44
Total responders | 15 | 83
*5 patients made disease free by surgery.

Twelve of these 18 patients either achieved a complete response (7 patients) or were made disease free by surgery after a partial response (5 patients, including one child) for a total complete response rate of 67%. A further 3 patients achieved a partial response, for an overall response rate of 83%. Of the 8 patients with metastatic disease, five responded (62%), three of them completely (37%). For the 10 study patients with the PDGF B gene rearrangement, there were 4 complete and 6 partial responses. The median duration of response in the Phase 2 study was 6.2 months, with a maximum duration of 24.3 months, while in the published literature it ranged between 4 weeks and more than 20 months.

14.9 Gastrointestinal Stromal Tumors

Unresectable and/or Malignant Metastatic GIST

Two open-label, randomized, multinational Phase 3 studies were conducted in patients with unresectable or metastatic malignant GIST. The two study designs were similar allowing a predefined combined analysis of safety and efficacy. A total of 1640 patients were enrolled into the two studies and randomized 1:1 to receive either 400 mg or 800 mg orally daily continuously until disease progression or unacceptable toxicity. Patients in the 400 mg daily treatment group who experienced disease progression were permitted to crossover to receive treatment with 800 mg daily. The studies were designed to compare response rates, progression-free survival and overall survival between the dose groups. Median age at patient entry was 60 years. Males comprised 58% of the patients enrolled. All patients had a pathologic diagnosis of CD117 positive unresectable and/or metastatic malignant GIST.

The primary objective of the two studies was to evaluate either progression-free survival (PFS) with a secondary objective of overall survival (OS) in one study or overall survival with a secondary objective of PFS in the other study. A planned analysis of both OS and PFS from the combined datasets from these two studies was conducted. Results from this combined analysis are shown in Table 26.

Table 26: Overall Survival, Progression-Free Survival and Tumor Response Rates in the Phase 3 GIST Trials
 | Gleevec 400 mg N = 818 | Gleevec 800 mg N = 822
Progression-free survival (months) Median | 18.9 | 23.2
95% CI | 17.4–21.2 | 20.8–24.9
Overall survival (months) | 49.0 | 48.7
95% CI | 45.3–60.0 | 45.3–51.6
Best overall tumor response Complete response Partial response | 43 (5.3%) 377 (46.1%) | 41 (5.0%) 402 (48.9%)
Abbreviation: GIST, gastrointestinal stromal tumors.

Median follow up for the combined studies was 37.5 months. There were no observed differences in overall survival between the treatment groups (p = 0.98). Patients who crossed over following disease progression from the 400 mg/day treatment group to the 800 mg/day treatment group (n = 347) had a 3.4 month median and a 7.7 month mean exposure to Gleevec following crossover.

One open-label, multinational Phase 2 study was conducted in patients with Kit (CD117) positive unresectable or metastatic malignant GIST. In this study, 147 patients were enrolled and randomized to receive either 400 mg or 600 mg orally every day for up to 36 months. The primary outcome of the study was objective response rate. Tumors were required to be measurable at entry in at least one site of disease, and response characterization was based on Southwestern Oncology Group (SWOG) criteria. There were no differences in response rates between the 2 dose groups. The response rate was 68.5% for the 400 mg group and 67.6% for the 600 mg group. The median time to response was 12 weeks (range was 3 to 98 weeks) and the estimated median duration of response is 118 weeks (95% CI: 86, not reached).

Adjuvant Treatment of GIST

In the adjuvant setting, Gleevec was investigated in a multicenter, double-blind, placebo-controlled, randomized trial involving 713 patients (Study 1). Patients were randomized one to one to Gleevec at 400 mg/day or matching placebo for 12 months. The ages of these patients ranged from 18 to 91 years. Patients were included who had a histologic diagnosis of primary GIST, expressing KIT protein by immunochemistry and a tumor size greater than or equal to 3 cm in maximum dimension with complete gross resection of primary GIST within 14 to 70 days prior to registration.

Recurrence-free survival (RFS) was defined as the time from date of randomization to the date of recurrence or death from any cause. In a planned interim analysis, the median follow up was 15 months in patients without a RFS event; there were 30 RFS events in the 12-month Gleevec arm compared to 70 RFS events in the placebo arm with a hazard ratio of 0.398 (95% CI: 0.259, 0.610), p less than 0.0001. After the interim analysis of RFS, 79 of the 354 patients initially randomized to the placebo arm were eligible to cross over to the 12-month Gleevec arm. Seventy-two of these 79 patients subsequently crossed over to Gleevec therapy. In an updated analysis, the median follow-up for patients without a RFS event was 50 months. There were 74 (21%) RFS events in the 12-month Gleevec arm compared to 98 (28%) events in the placebo arm with a hazard ratio of 0.718 (95% CI: 0.531-0.971) (Figure 3). The median follow-up for OS in patients still living was 61 months. There were 26 (7%) and 33 (9%) deaths in the 12-month Gleevec and placebo arms, respectively with a hazard ratio of 0.816 (95% CI: 0.488-1.365).

Figure 3: Study 1 Recurrence-Free Survival (ITT Population)

A second randomized, multicenter, open-label, Phase 3 trial in the adjuvant setting (Study 2) compared 12 months of Gleevec treatment to 36 months of Gleevec treatment at 400 mg/day in adult patients with KIT (CD117) positive GIST after surgical resection with one of the following: tumor diameter greater than 5 cm and mitotic count greater than 5/50 high power fields (HPF), or tumor diameter greater than 10 cm and any mitotic count, or tumor of any size with mitotic count greater than 10/50 HPF, or tumors ruptured into the peritoneal cavity. There were a total of 397 patients randomized in the trial with 199 patients on the 12-month treatment arm and 198 patients on the 36-month treatment arm. The median age was 61 years (range, 22 to 84 years).

RFS was defined as the time from date of randomization to the date of recurrence or death from any cause. The median follow-up for patients without a RFS event was 42 months. There were 84 (42%) RFS events in the 12-month treatment arm and 50 (25%) RFS events in the 36-month treatment arm. Thirty-six months of Gleevec treatment significantly prolonged RFS compared to 12 months of Gleevec treatment with a hazard ratio of 0.46 (95% CI: 0.32, 0.65), p less than 0.0001 (Figure 4).

The median follow-up for overall survival (OS) in patients still living was 48 months. There were 25 (13%) deaths in the 12-month treatment arm and 12 (6%) deaths in the 36-month treatment arm. Thirty-six months of Gleevec treatment significantly prolonged OS compared to 12 months of Gleevec treatment with a hazard ratio of 0.45 (95% CI: 0.22, 0.89), p = 0.0187 (Figure 5).

Figure 4: Study 2 Recurrence-Free Survival (ITT Population)

Figure 5: Study 2 Overall Survival (ITT Population)

15 REFERENCES

OSHA Hazardous Drugs. OSHA. [Accessed on 20-September- 2013, from http://www.osha.gov/SLTC/hazardousdrugs/index.html]

16 HOW SUPPLIED/STORAGE AND HANDLING

Gleevec film-coated tablets are supplied as 100 mg and 400 mg tablets for oral administration. Each 100 mg tablet contains 119.5 mg of imatinib mesylate equivalent to 100 mg of imatinib free base. Each 400 mg tablet contains 478 mg of imatinib mesylate equivalent to 400 mg of imatinib free base.

- 100-mg tablets

Very dark yellow to brownish orange, film-coated tablets, round, biconvex with bevelled edges, debossed with “NVR” on one side, and “SA” with score on the other side.

Bottles of 90 tablets…………………………………NDC 0078-0401-34

- 400-mg tablets

Very dark yellow to brownish orange, film-coated tablets, ovaloid, biconvex with bevelled edges, debossed with “gleevec” on one side and score on the other side.

Unit Dose (blister pack of 30) ………………………NDC 0078-0649-30

Unit Dose (carton box including 3 blister packs of 10)…………NDC 0078-0649-13

Very dark yellow to brownish orange, film-coated tablets, ovaloid, biconvex with bevelled edges, debossed with “400” on one side and score on the other side with “SL” on each side of the score.

Unit Dose (carton box including 3 blister packs of 10)………....NDC 0078-1490-13

Storage and Handling

Store at 20°C to 25°C (68°F to 77°F); excursions permitted between 15°C and 30°C (59°F and 86°F) [see USP Controlled Room Temperature]. Protect from moisture.

Dispense in a tight container, USP.

Do not crush Gleevec tablets. Avoid direct contact of crushed tablets with the skin or mucous membranes. If such contact occurs, wash thoroughly as outlined in the references. Avoid exposure to crushed tablets.

17 PATIENT COUNSELING INFORMATION

Dosing and Administration

Advise patients to take Gleevec exactly as prescribed, not to change their dose or to stop taking Gleevec unless they are told to do so by their doctor. If the patient missed a dose of Gleevec, the patient should take the next scheduled dose at its regular time. The patient should not take two doses at the same time. Advise patients to take Gleevec with a meal and a large glass of water [see Dosage and Administration (2.1)].

Fluid Retention and Edema

Inform patients of the possibility of developing edema and fluid retention. Advise patients to contact their health care provider if unexpected rapid weight gain occurs [see Warnings and Precautions (5.1)].

Hepatotoxicity

Inform patients of the possibility of developing liver function abnormalities and serious hepatic toxicity. Advise patients to immediately contact their health care provider if signs of liver failure occur, including jaundice, anorexia, bleeding, or bruising [see Warnings and Precautions (5.4)].

Pregnancy and Breastfeeding

Advise patients to inform their doctor if they are or think they may be pregnant. Advise women of reproductive potential to avoid becoming pregnant while taking Gleevec. Female patients of reproductive potential taking Gleevec should use highly effective contraception during treatment and for fourteen days after stopping treatment with Gleevec [see Use in Specific Populations (8.3)]. Avoid breastfeeding during treatment and for 1 month after the last dose [see Use in Specific Populations (8.2)].

Drug Interactions

Gleevec and certain other medicines, such as warfarin, erythromycin, and phenytoin, including over-the-counter medications, such as herbal products, can interact with each other. Advise patients to tell their doctor if they are taking or plan to take iron supplements. Avoid grapefruit juice and other foods known to inhibit CYP3A4 while taking Gleevec [see Drug Interactions (7)].

Pediatric

Advise patients that growth retardation has been reported in children and pre-adolescents receiving Gleevec. The long term effects of prolonged treatment with Gleevec on growth in children are unknown. Therefore, closely monitor growth in children under Gleevec treatment [see Warnings and Precautions (5.11)].

Driving and Using Machines

Advise patients that they may experience side effects, such as dizziness, blurred vision, or somnolence during treatment with Gleevec. Therefore, caution patients about driving a car or operating machinery [see Warnings and Precautions (5.13)].

Distributed by
Novartis Pharmaceuticals Corporation
East Hanover, New Jersey 07936

© Novartis

T2026-01

PRINCIPAL DISPLAY PANEL

NDC 0078-0401-34

Rx only

Gleevec®
(imatinib mesylate)

Tablets

100 mg

Each tablet contains 119.5 mg
of imatinib mesylate equivalent
to 100 mg of imatinib free base.

90 Tablets

NOVARTIS

PRINCIPAL DISPLAY PANEL

NDC 0078-0649-13

Rx Only

gleevec®
(imatinib mesylate) tablets

400 mg per tablet

Each tablet contains 478 mg of imatinib mesylate
equivalent to 400 mg of imatinib free base.

30 Tablets

NOVARTIS

PRINCIPAL DISPLAY PANEL

NDC 0078-1490-13

Rx Only

gleevec®
(imatinib mesylate) tablets

400 mg per tablet

Each tablet contains 478 mg of imatinib mesylate
equivalent to 400 mg of imatinib free base.

30 Tablets

NOVARTIS